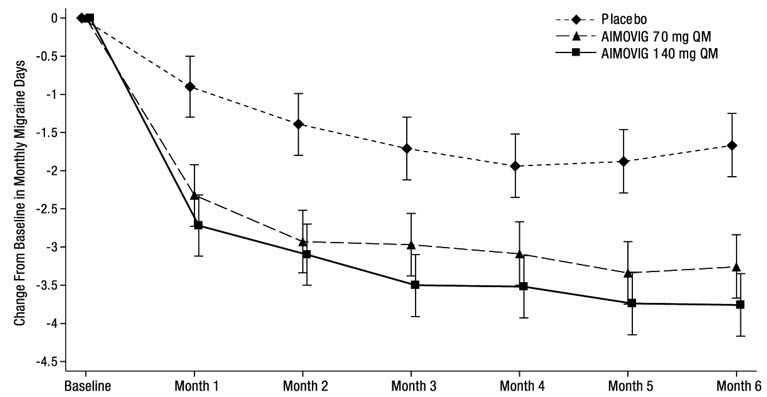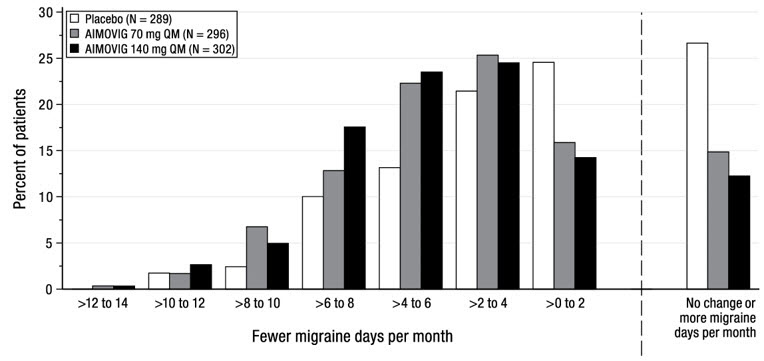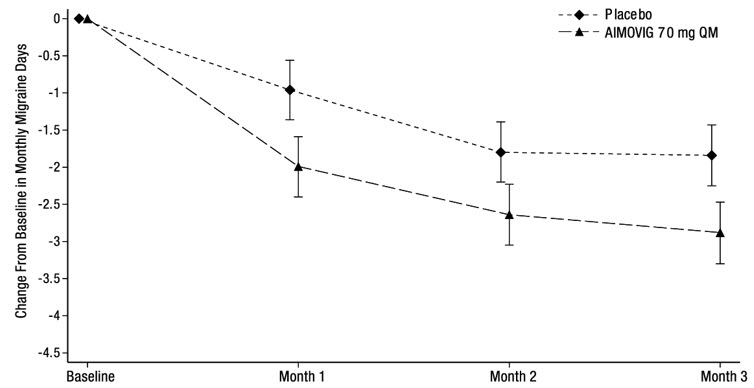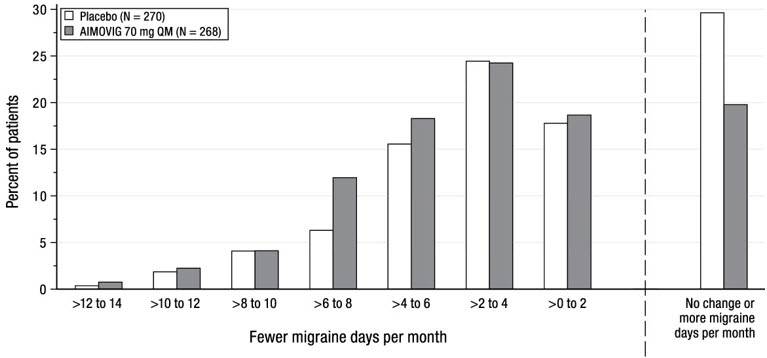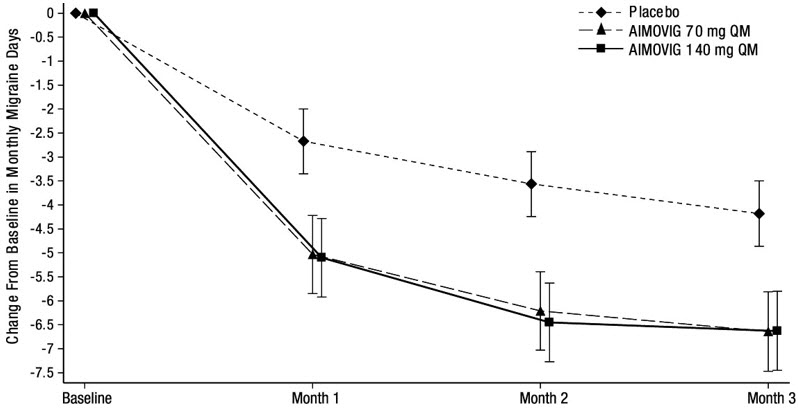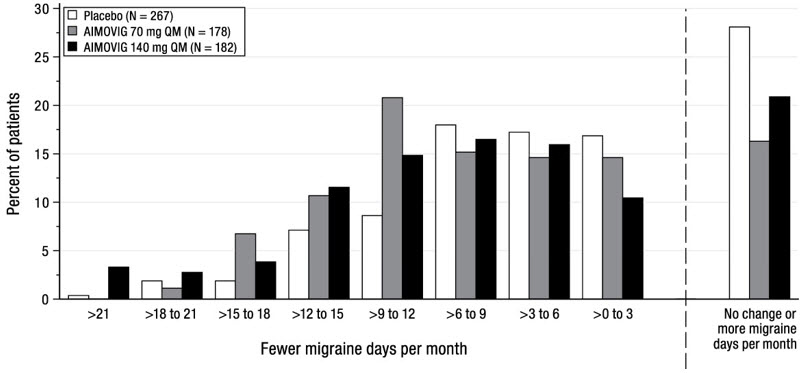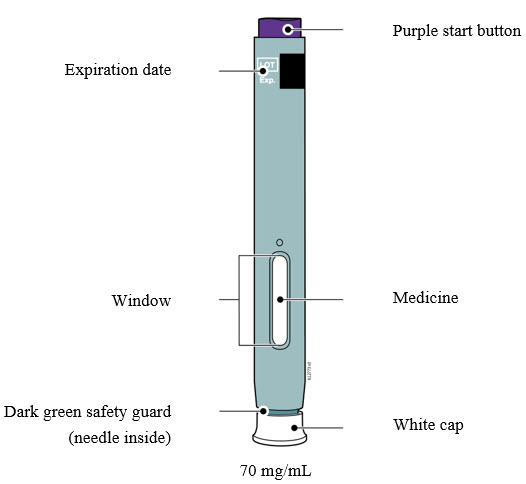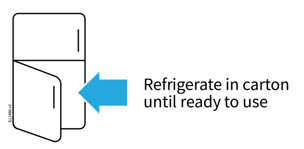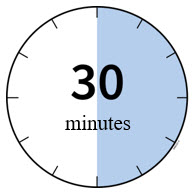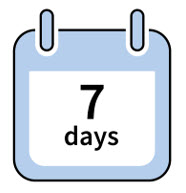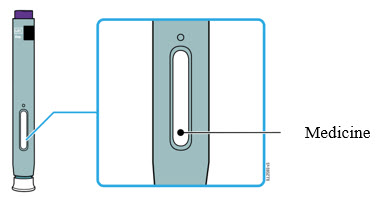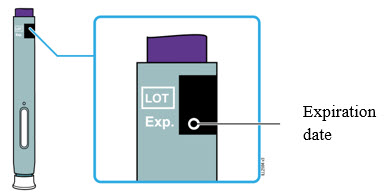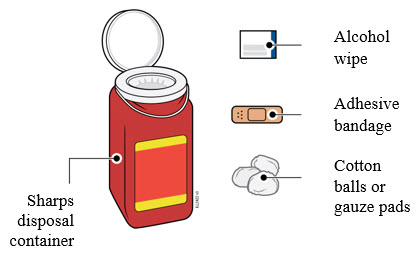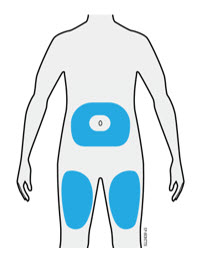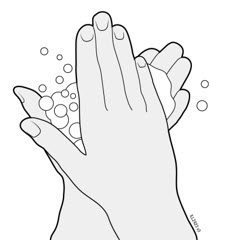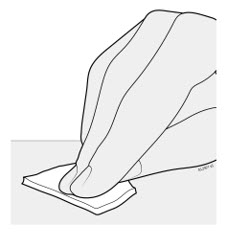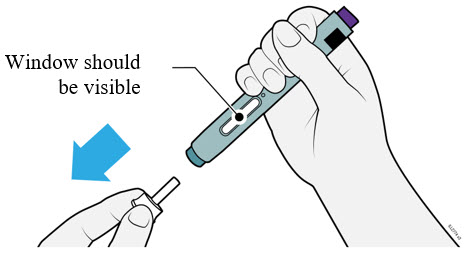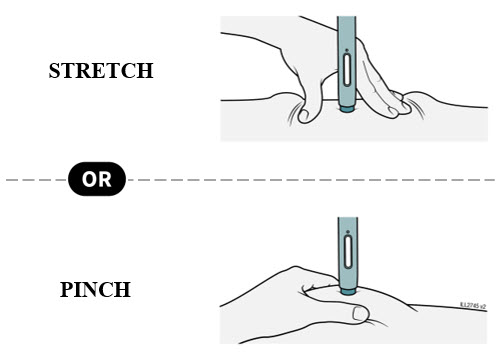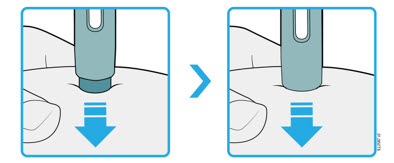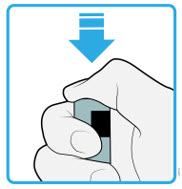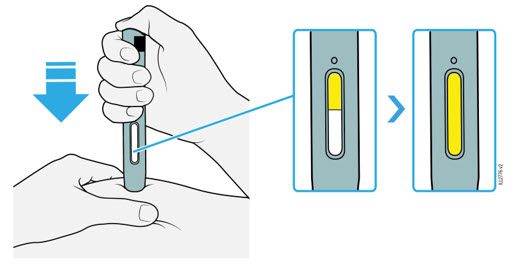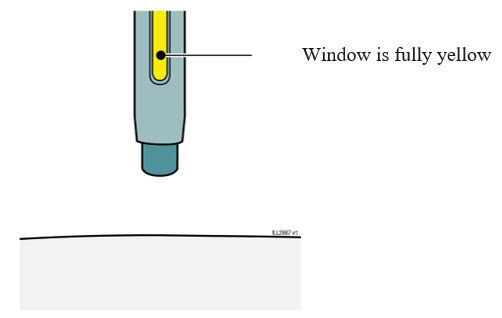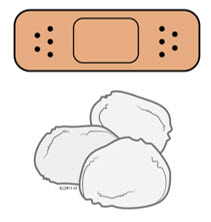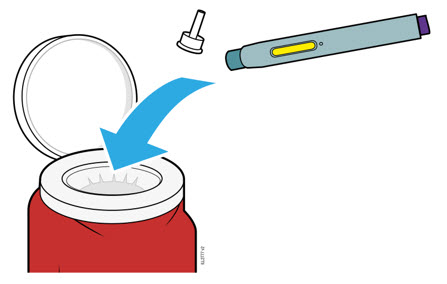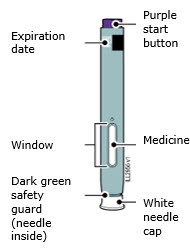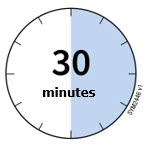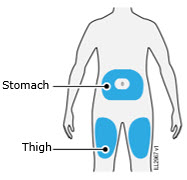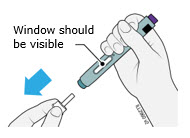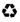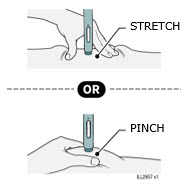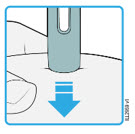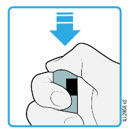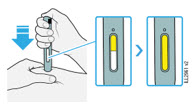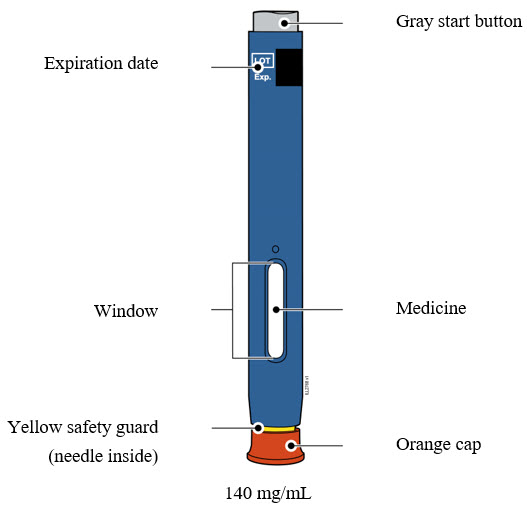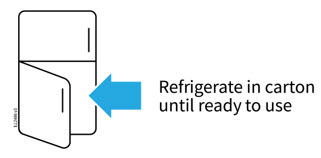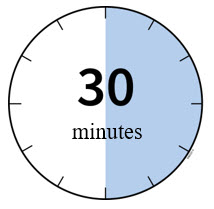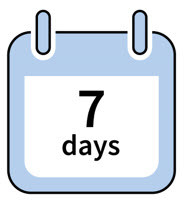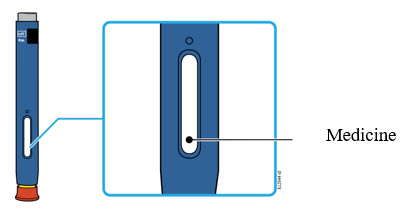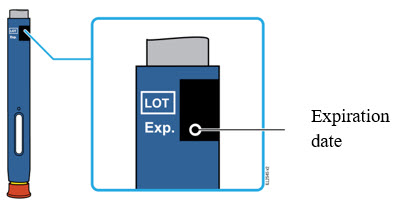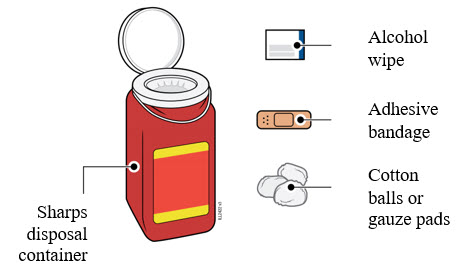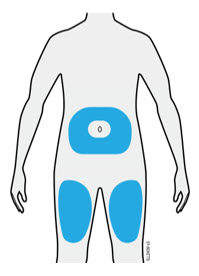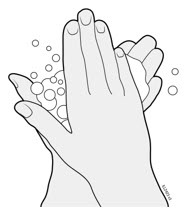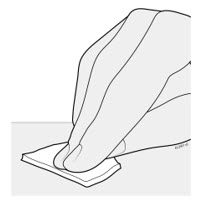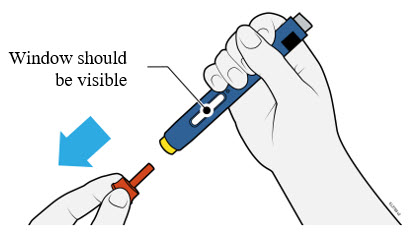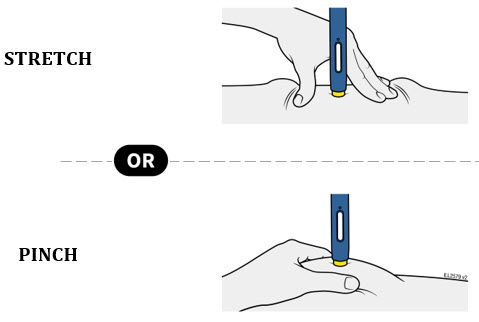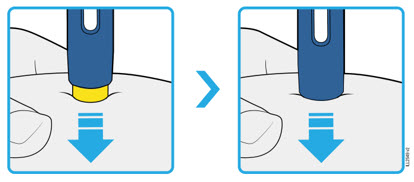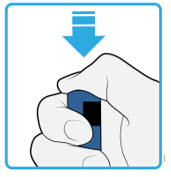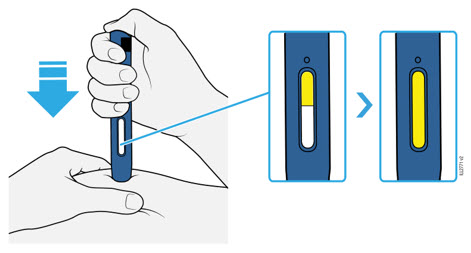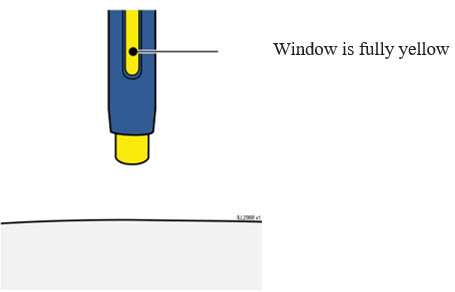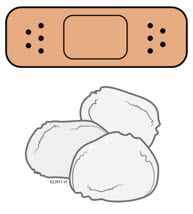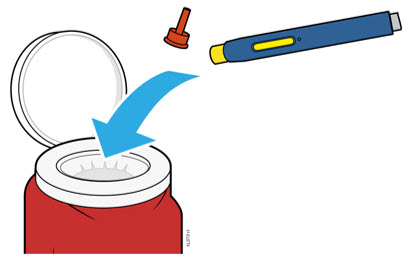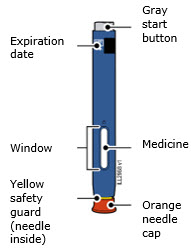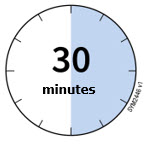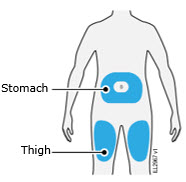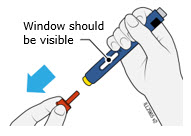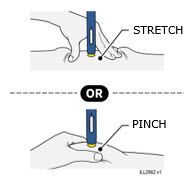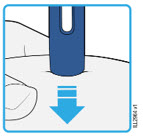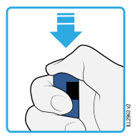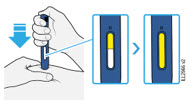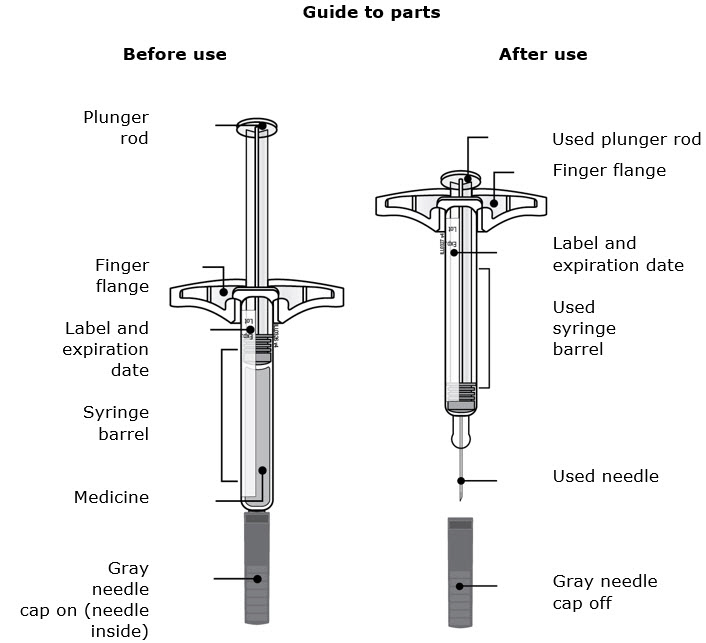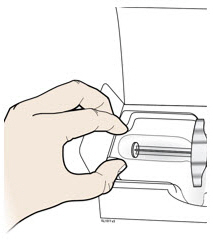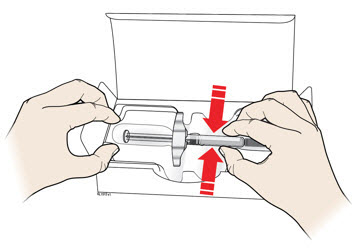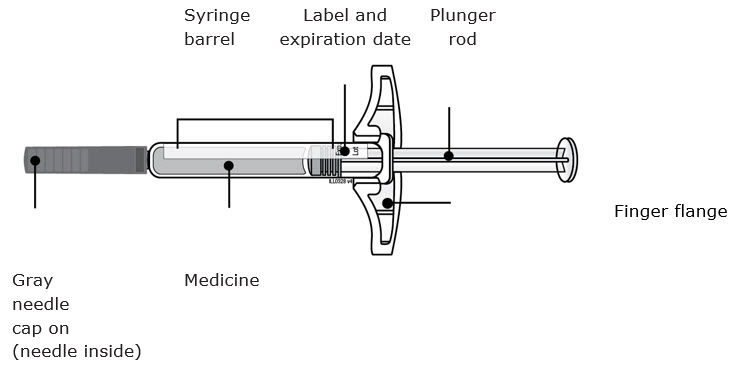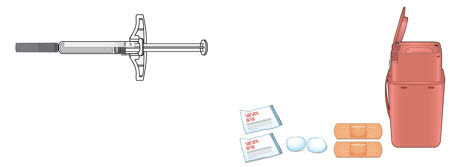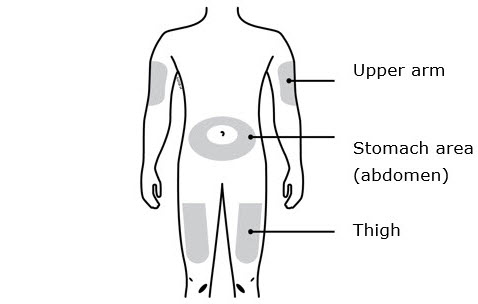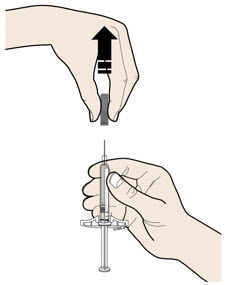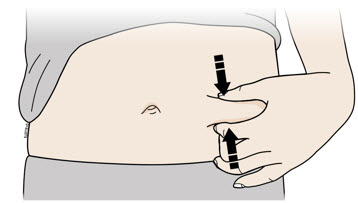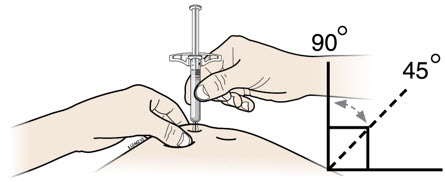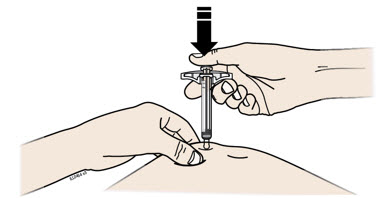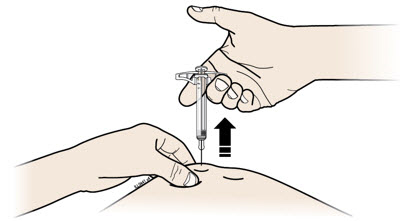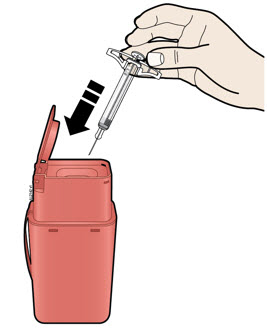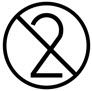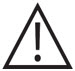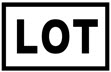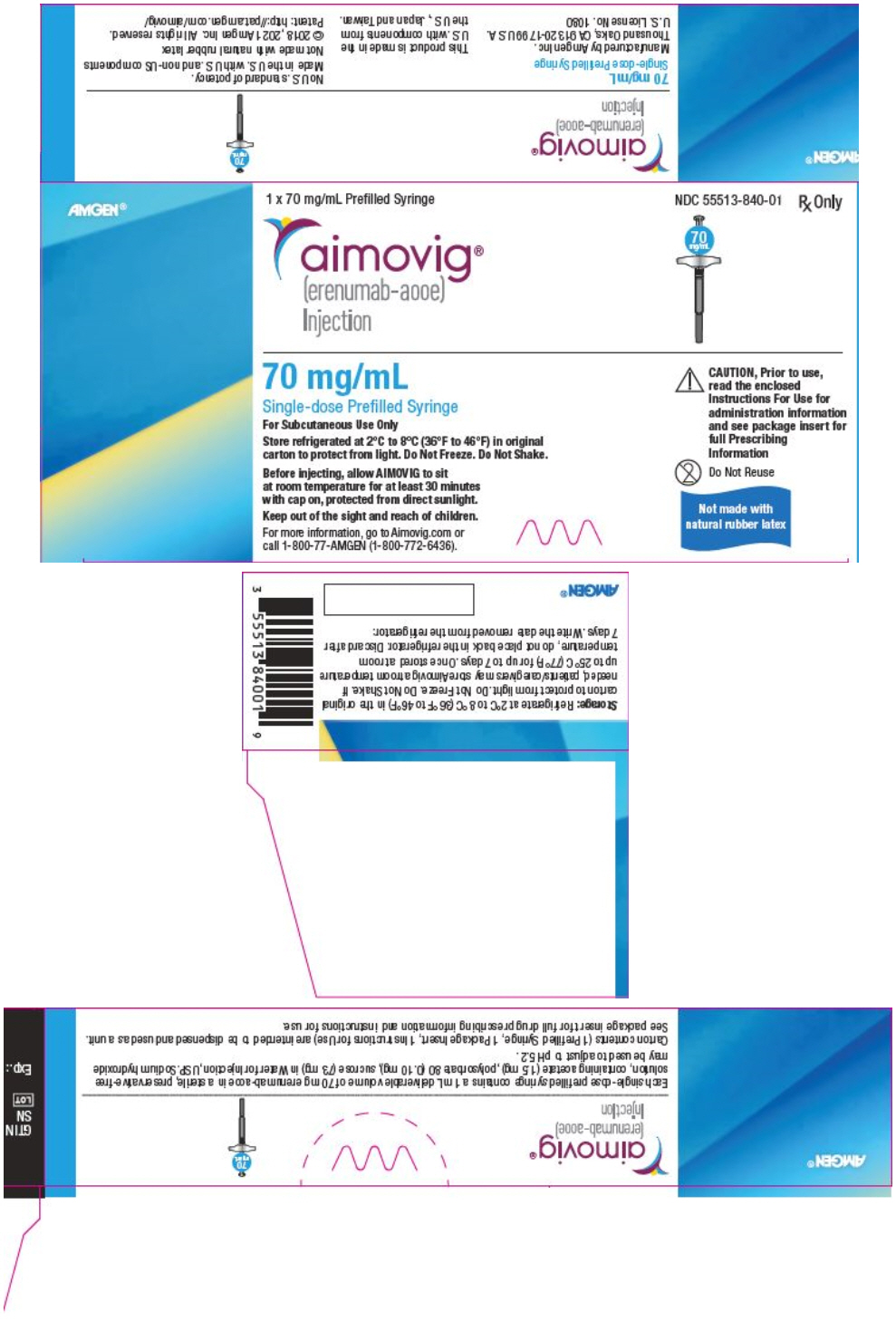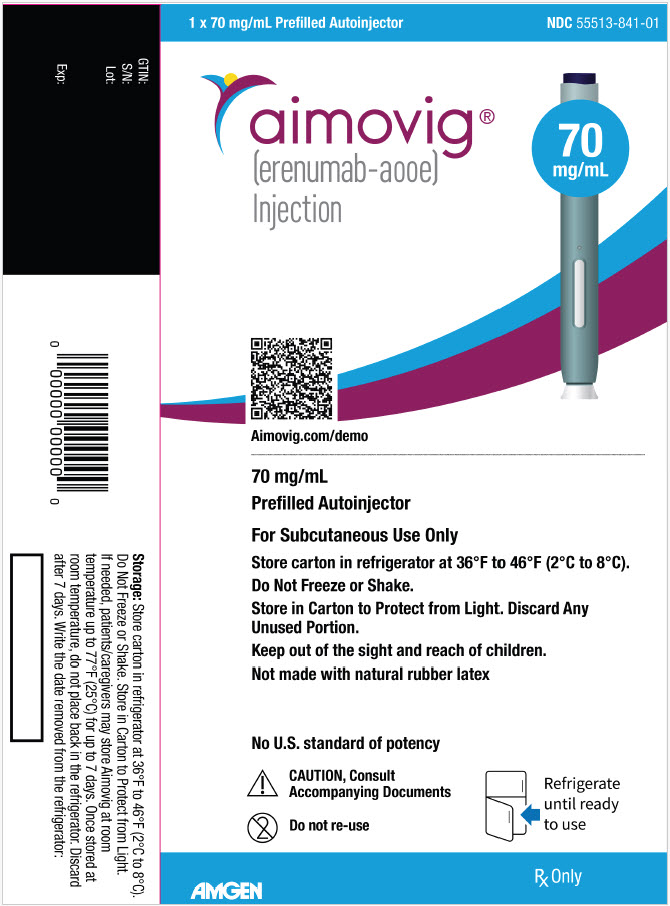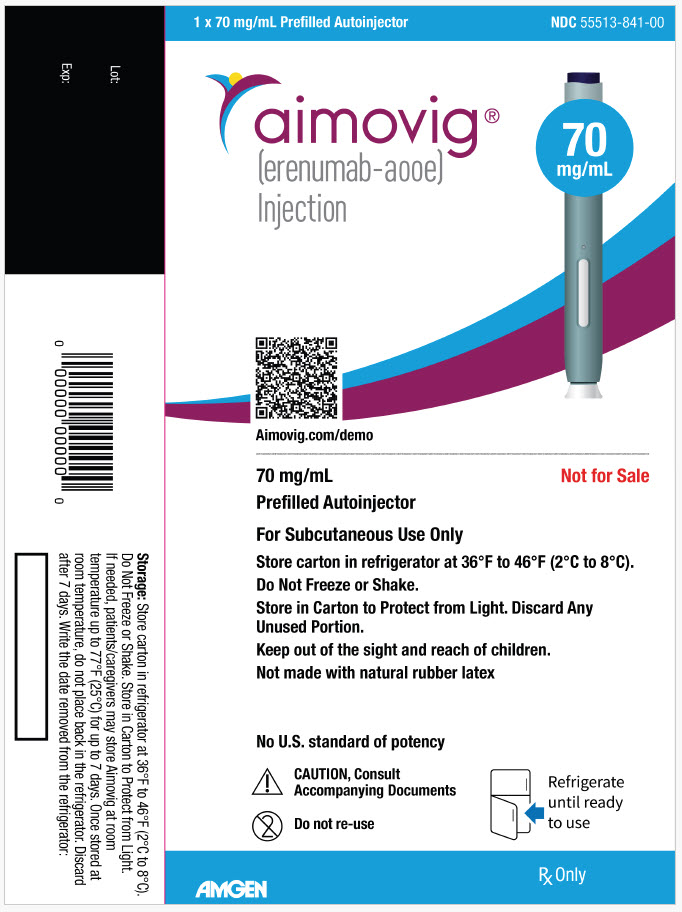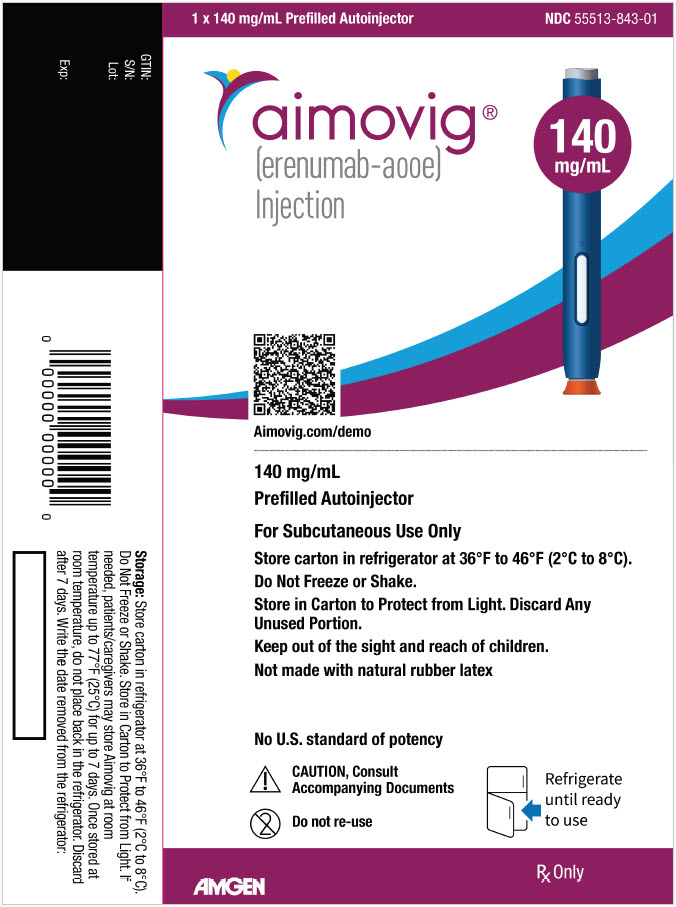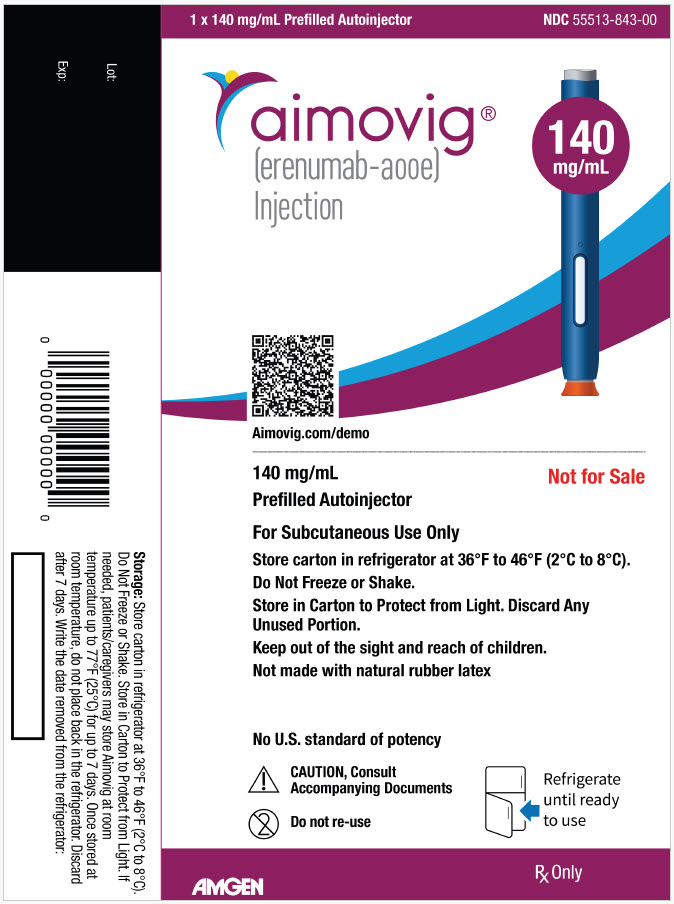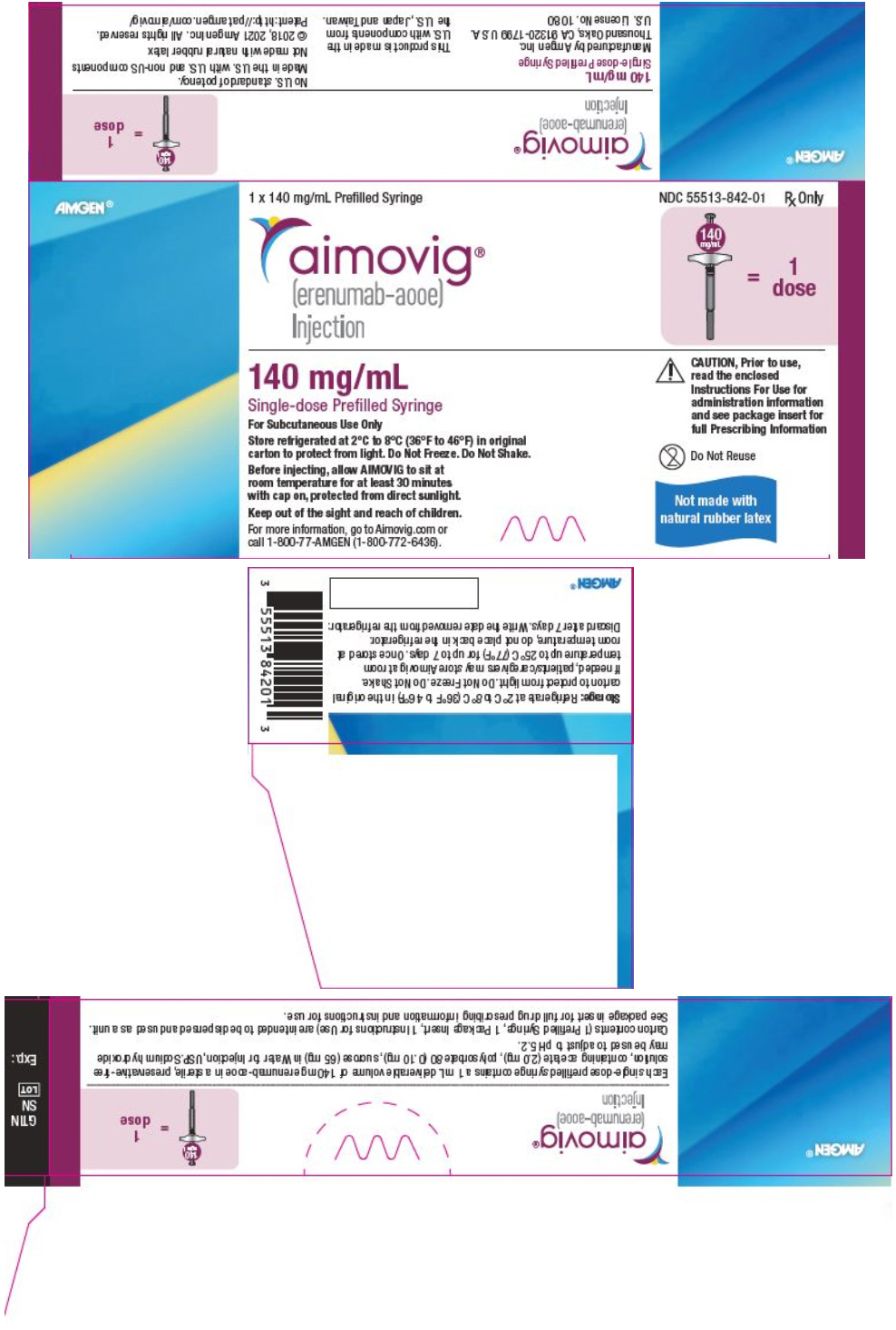 DRUG LABEL: AIMOVIG
NDC: 55513-840 | Form: INJECTION
Manufacturer: Amgen Inc
Category: prescription | Type: HUMAN PRESCRIPTION DRUG LABEL
Date: 20250619

ACTIVE INGREDIENTS: ERENUMAB 70 mg/1 mL
INACTIVE INGREDIENTS: ACETATE ION 1.5 mg/1 mL; SUCROSE 73 mg/1 mL; POLYSORBATE 80 0.1 mg/1 mL

HIGHLIGHTS OF PRESCRIBING INFORMATION

These highlights do not include all the information needed to use AIMOVIG safely and effectively. See full prescribing information for AIMOVIG.
AIMOVIG® (erenumab-aooe) injection, for subcutaneous use
Initial U.S. Approval: 2018

RECENT MAJOR CHANGES

Warnings and Precautions (5.4) | 3/2025

1 INDICATIONS AND USAGE

AIMOVIG is a calcitonin gene-related peptide receptor antagonist indicated for the preventive treatment of migraine in adults. (1)

2 DOSAGE AND ADMINISTRATION

- For subcutaneous use only (2.1, 2.2)
- Recommended dosage is 70 mg once monthly; some patients may benefit from a dosage of 140 mg once monthly (2.1)
- Administer in the abdomen, thigh, or upper arm subcutaneously (2.2)
- See Dosage and Administration for important administration instructions (2.2)

3 DOSAGE FORMS AND STRENGTHS

- Injection: 70 mg/mL solution in a single-dose prefilled SureClick® autoinjector (3)
- Injection: 140 mg/mL solution in a single-dose prefilled SureClick® autoinjector (3)
- Injection: 70 mg/mL solution in a single-dose prefilled syringe (3)
- Injection: 140 mg/mL solution in a single-dose prefilled syringe (3)

4 CONTRAINDICATIONS

AIMOVIG is contraindicated in patients with serious hypersensitivity to erenumab-aooe or to any of the excipients. (4)

5 WARNINGS AND PRECAUTIONS

- Hypersensitivity Reactions: If a serious hypersensitivity reaction occurs, discontinue administration of AIMOVIG and initiate appropriate therapy. Hypersensitivity reactions can occur within hours to more than one week after administration. (5.1)
- Constipation with Serious Complications: Serious complications of constipation may occur. (5.2)
- Hypertension: New-onset or worsening of pre-existing hypertension may occur. (5.3)
- Raynaud's Phenomenon: New-onset or worsening of pre-existing Raynaud's phenomenon may occur. (5.4)

6 ADVERSE REACTIONS

The most common adverse reactions in AIMOVIG clinical studies (occurring in at least 3% of treated patients and more often than placebo) are injection site reactions and constipation. (6.1)

To report SUSPECTED ADVERSE REACTIONS, contact Amgen Medical Information at 1-800-77-AMGEN (1-800-772-6436) or FDA at 1-800-FDA-1088 or www.fda.gov/medwatch.

FULL PRESCRIBING INFORMATION

1 INDICATIONS AND USAGE

AIMOVIG is indicated for the preventive treatment of migraine in adults.

2 DOSAGE AND ADMINISTRATION

2.1 Recommended Dosing

The recommended dosage of AIMOVIG is 70 mg injected subcutaneously once monthly. Some patients may benefit from a dosage of 140 mg injected subcutaneously once monthly.

If a dose of AIMOVIG is missed, administer as soon as possible. Thereafter, AIMOVIG can be scheduled monthly from the date of the last dose.

2.2 Important Administration Instructions

AIMOVIG is for subcutaneous use only.

AIMOVIG is intended for patient self-administration. Prior to use, provide proper training to patients and/or caregivers on how to prepare and administer AIMOVIG using the single-dose prefilled autoinjector or single-dose prefilled syringe, including aseptic technique [see Instructions for Use]:

- Prior to subcutaneous administration, allow AIMOVIG to sit at room temperature for at least 30 minutes protected from direct sunlight [see How Supplied/Storage and Handling (16.2)]. This is important for administering the entire dose and helps minimize discomfort. Do not warm by using a heat source such as hot water or a microwave.
- Do not shake the product.
- Inspect visually for particulate matter and discoloration prior to administration [see Dosage Forms and Strengths (3)]. Do not use if the solution is cloudy or discolored or contains flakes or particles.
- Administer AIMOVIG in the abdomen, thigh, or upper arm subcutaneously. Do not inject into areas where the skin is tender, bruised, red, or hard.
- Both prefilled autoinjector and prefilled syringe are single-dose and deliver the entire contents.

3 DOSAGE FORMS AND STRENGTHS

AIMOVIG is a sterile, clear to opalescent, colorless to light yellow solution available as follows:

- Injection: 70 mg/mL in a single-dose prefilled SureClick® autoinjector
- Injection: 140 mg/mL in a single-dose prefilled SureClick® autoinjector
- Injection: 70 mg/mL in a single-dose prefilled syringe
- Injection: 140 mg/mL in a single-dose prefilled syringe

4 CONTRAINDICATIONS

AIMOVIG is contraindicated in patients with serious hypersensitivity to erenumab-aooe or to any of the excipients. Reactions have included anaphylaxis and angioedema [see Warnings and Precautions (5.1)].

5 WARNINGS AND PRECAUTIONS

5.1 Hypersensitivity Reactions

Hypersensitivity reactions, including rash, angioedema, and anaphylaxis, have been reported with AIMOVIG in postmarketing experience. Most hypersensitivity reactions were not serious and occurred within hours of administration, although some occurred more than one week after administration. If a serious or severe hypersensitivity reaction occurs, discontinue administration of AIMOVIG and initiate appropriate therapy [see Contraindications (4), and Patient Counseling Information (17)].

5.2 Constipation with Serious Complications

Constipation with serious complications has been reported following the use of AIMOVIG in the postmarketing setting. There were cases that required hospitalization, including cases where surgery was necessary. In a majority of these cases, the onset of constipation was reported after the first dose of AIMOVIG; however, patients have also presented with constipation later on in treatment. AIMOVIG was discontinued in most reported cases of constipation with serious complications. Constipation was one of the most common (up to 3%) adverse reactions reported in clinical studies [see Adverse Reactions (6.1)].

Monitor patients treated with AIMOVIG for severe constipation and manage as clinically appropriate [see Patient Counseling Information (17)]. The concurrent use of medications associated with decreased gastrointestinal motility may increase the risk for more severe constipation and the potential for constipation-related complications.

5.3 Hypertension

Development of hypertension and worsening of pre-existing hypertension have been reported following the use of AIMOVIG in the postmarketing setting. Many of the patients had pre-existing hypertension or risk factors for hypertension. There were cases requiring pharmacological treatment and, in some cases, hospitalization. Hypertension may occur at any time during treatment but was most frequently reported within seven days of dose administration. In the majority of the cases, the onset or worsening of hypertension was reported after the first dose. AIMOVIG was discontinued in many of the reported cases.

Monitor patients treated with AIMOVIG for new-onset hypertension, or worsening of pre-existing hypertension, and consider whether discontinuation of AIMOVIG is warranted if evaluation fails to establish an alternative etiology.

5.4 Raynaud's Phenomenon

Development of Raynaud's phenomenon and recurrence or worsening of pre-existing Raynaud's phenomenon have been reported in the postmarketing setting following the use of CGRP antagonists, including AIMOVIG. In reported cases with monoclonal antibody CGRP antagonists, symptom onset occurred a median of 71 days following dosing. Many of the cases reported serious outcomes, including hospitalizations and disability, generally related to debilitating pain. In most reported cases, discontinuation of the CGRP antagonist resulted in resolution of symptoms.

AIMOVIG should be discontinued if signs or symptoms of Raynaud's phenomenon develop, and patients should be evaluated by a healthcare provider if symptoms do not resolve. Patients with a history of Raynaud's phenomenon should be monitored for, and informed about the possibility of, worsening or recurrence of signs and symptoms.

6 ADVERSE REACTIONS

The following serious adverse reactions are described below and elsewhere in the labeling:

- Hypersensitivity Reactions [see Warnings and Precautions (5.1)]
- Constipation with Serious Complications [see Warnings and Precautions (5.2)]
- Hypertension [see Warnings and Precautions (5.3)]
- Raynaud's Phenomenon [see Warnings and Precautions (5.4)]

6.1 Clinical Trials Experience

Because clinical trials are conducted under widely varying conditions, adverse reaction rates observed in the clinical trials of a drug cannot be directly compared to rates in the clinical trials of another drug and may not reflect the rates observed in clinical practice.

The safety of AIMOVIG has been evaluated in 2537 patients with migraine who received at least one dose of AIMOVIG, representing 3040.2 patient-years of exposure. Of these, 2271 patients were exposed to 70 mg or 140 mg once monthly for at least 6 months, 1305 patients were exposed for at least 12 months, and 216 patients were exposed through 5 years.

In placebo-controlled clinical studies (Studies 1, 2, and 3) of 2184 patients, 787 patients received at least one dose of AIMOVIG 70 mg once monthly, 507 patients received at least one dose of AIMOVIG 140 mg once monthly, and 890 patients received placebo during 3 months or 6 months of double-blind treatment [see Clinical Studies (14)]. Approximately 84% were female, 91% were white, and the mean age was 42 years at study entry.

The most common adverse reactions (incidence ≥ 3% and more often than placebo) in the migraine studies were injection site reactions and constipation. Table 1 summarizes the adverse reactions that occurred during the first 3 months in the migraine studies (Studies 1, 2, and 3).

Table 1: Adverse Reactions Occurring with an Incidence of at Least 2% for Either Dose of AIMOVIG and at Least 2% Greater than Placebo During the First 3 Months in Studies 1, 2, and 3
Adverse Reaction | AIMOVIG 70 mg Once Monthly N = 787 % | AIMOVIG 140 mg Once Monthly N = 507 % | Placebo N = 890 %
Injection site reactions [Injection site reactions include multiple adverse reactions related terms, such as injection site pain and injection site erythema.] , [The rate of injection site reactions reported in Table 1 is with the prefilled syringe.] | 6 | 5 | 3
Constipation | 1 | 3 | 1
Cramps, muscle spasms | < 1 | 2 | < 1

In Studies 1, 2, and 3, 1.3% of patients treated with AIMOVIG 70 mg or 140 mg discontinued double-blind treatment because of adverse events. The most frequent injection site reactions were injection site pain, injection site erythema, and injection site pruritus.

6.2 Postmarketing Experience

The following adverse reactions have been identified during postapproval use of AIMOVIG. Because these reactions are reported voluntarily from a population of uncertain size, it is not always possible to reliably estimate their frequency or establish a causal relationship to drug exposure.

Immune System Disorders: Hypersensitivity reactions, including rash, angioedema, and anaphylaxis [see Warnings and Precautions (5.1)].

Gastrointestinal Disorders: Constipation with serious complications [see Warnings and Precautions (5.2)], oral mucosal ulceration.

Skin and Subcutaneous Tissue Disorders: Rash, alopecia.

Vascular Disorders: Hypertension [see Warnings and Precautions (5.3)], Raynaud's Phenomenon [see Warnings and Precautions (5.4)].

8 USE IN SPECIFIC POPULATIONS

8.1 Pregnancy

Pregnancy Exposure Registry

There is a pregnancy exposure registry that monitors pregnancy outcomes in women exposed to AIMOVIG during pregnancy. Patients should be encouraged to enroll by calling 1-833-244-4083 or visiting https://www.genesispregnancyregistry.com/.

Risk Summary

There are no adequate data on the developmental risk associated with the use of AIMOVIG in pregnant women. No adverse effects on offspring were observed when pregnant monkeys were administered erenumab-aooe throughout gestation [see Data]. Serum erenumab-aooe exposures in pregnant monkeys were greater than those in humans at clinical doses.

In the U.S. general population, the estimated background risk of major birth defects and miscarriage in clinically recognized pregnancies is 2%-4% and 15%-20%, respectively. The estimated rate of major birth defects (2.2%-2.9%) and miscarriage (17%) among deliveries to women with migraine are similar to rates reported in women without migraine.

Clinical Considerations

Disease-Associated Maternal and/or Embryo/Fetal Risk

Published data have suggested that women with migraine may be at increased risk of preeclampsia and gestational hypertension during pregnancy.

Data

Animal Data

In a study in which female monkeys were administered erenumab-aooe (0 or 50 mg/kg) twice weekly by subcutaneous injection throughout pregnancy (gestation day 20-22 to parturition), no adverse effects on offspring were observed. Serum erenumab-aooe exposures (AUC) in pregnant monkeys were approximately 20 times that in humans at a dose of 140 mg once monthly.

8.2 Lactation

Risk Summary

There are no data on the presence of erenumab-aooe in human milk, the effects on the breastfed infant, or the effects on milk production. The developmental and health benefits of breastfeeding should be considered along with the mother's clinical need for AIMOVIG and any potential adverse effects on the breastfed infant from AIMOVIG or from the underlying maternal condition.

8.4 Pediatric Use

Safety and effectiveness in pediatric patients have not been established.

8.5 Geriatric Use

Clinical studies of AIMOVIG did not include sufficient numbers of patients aged 65 and over to determine whether they respond differently from younger patients. In general, dose selection for an elderly patient should be cautious, usually starting at the low end of the dosing range, reflecting the greater frequency of decreased hepatic, renal, or cardiac function, and of concomitant disease or other drug therapy.

11 DESCRIPTION

Erenumab-aooe is a human immunoglobulin G2 (IgG2) monoclonal antibody that has high affinity binding to the calcitonin gene-related peptide receptor. Erenumab-aooe is produced using recombinant DNA technology in Chinese hamster ovary (CHO) cells. It is composed of 2 heavy chains, each containing 456 amino acids, and 2 light chains of the lambda subclass, each containing 216 amino acids, with an approximate molecular weight of 150 kDa.

AIMOVIG (erenumab-aooe) injection is supplied as a sterile, preservative-free, clear to opalescent, colorless to light yellow solution for subcutaneous administration. Each 1 mL 70 mg single-dose prefilled autoinjector and 70 mg single-dose prefilled glass syringe contains 70 mg erenumab-aooe, acetate (1.5 mg), polysorbate 80 (0.10 mg), and sucrose (73 mg). Each 1 mL 140 mg single-dose prefilled autoinjector and 140 mg single-dose prefilled glass syringe contains 140 mg erenumab-aooe, acetate (2.0 mg), polysorbate 80 (0.10 mg), and sucrose (65 mg). Enclosed within the autoinjector is a single-dose, prefilled glass syringe. The solution of AIMOVIG has a pH of 5.2.

12 CLINICAL PHARMACOLOGY

12.1 Mechanism of Action

Erenumab-aooe is a human monoclonal antibody that binds to the calcitonin gene-related peptide (CGRP) receptor and antagonizes CGRP receptor function.

12.2 Pharmacodynamics

In a randomized, double-blind, placebo-controlled study in healthy volunteers, concomitant administration of erenumab-aooe (140 mg intravenous, single-dose) with sumatriptan (12 mg subcutaneous, given as two 6 mg doses separated by one hour) had no effect on resting blood pressure compared with sumatriptan alone. AIMOVIG is for subcutaneous use only.

12.3 Pharmacokinetics

Erenumab-aooe exhibits non-linear kinetics as a result of binding to the CGRP receptor. The Cmax mean and AUClast mean following subcutaneous administration of a 70 mg once monthly and a 140 mg once monthly dose in healthy volunteers or migraine patients are included in Table 2.

Less than 2-fold accumulation was observed in trough serum concentrations (Cmin) for episodic and chronic migraine patients following subcutaneous administration of 70 mg once monthly and 140 mg once monthly doses (see Table 2). Serum trough concentrations approached steady state by 3 months of dosing. The effective half-life of erenumab-aooe is 28 days.

Table 2: Pharmacokinetic Parameters of AIMOVIG
 | AIMOVIG 70 mg Subcutaneously Once Monthly | AIMOVIG 140 mg Subcutaneously Once Monthly
Cmax mean (SD) [SD = standard deviation] , [from a single-dose study] | 6.1 (2.1) mcg/mL | 15.8 (4.8) mcg/mL
AUClast mean (SD), | 159 (58) day*mcg/mL | 505 (139) day*mcg/mL
Cmin (SD)
Episodic migraine | 5.7 (3.1) mcg/mL | 12.8 (6.5) mcg/mL
Chronic migraine | 6.2 (2.9) mcg/mL | 14.9 (6.5) mcg/mL

Absorption

Following a single subcutaneous dose of 70 mg or 140 mg erenumab-aooe administered to healthy adults, median peak serum concentrations were attained in approximately 6 days, and estimated absolute bioavailability was 82%.

Distribution

Following a single 140 mg intravenous dose, the mean (SD) volume of distribution during the terminal phase (Vz) was estimated to be 3.86 (0.77) L.

Metabolism and Excretion

Two elimination phases were observed for erenumab-aooe. At low concentrations, the elimination is predominantly through saturable binding to target (CGRP receptor), while at higher concentrations the elimination of erenumab-aooe is largely through a non-specific, non-saturable proteolytic pathway.

Specific Populations

The pharmacokinetics of erenumab-aooe were not affected by age, gender, race, or subtypes of migraine spectrum (episodic or chronic migraine) based on population pharmacokinetics analysis.

Patients with Renal or Hepatic Impairment

Population pharmacokinetic analysis of integrated data from the AIMOVIG clinical studies did not reveal a difference in the pharmacokinetics of erenumab-aooe in patients with mild or moderate renal impairment relative to those with normal renal function. Patients with severe renal impairment (eGFR < 30 mL/min/1.73 m^2) have not been studied. No dedicated clinical studies were conducted to evaluate the effect of hepatic impairment or renal impairment on the pharmacokinetics of erenumab-aooe. Renal or hepatic impairment is not expected to affect pharmacokinetics of erenumab-aooe.

Drug Interaction Studies

P450 Enzymes

Erenumab-aooe is not metabolized by cytochrome P450 enzymes; therefore, interactions with concomitant medications that are substrates, inducers, or inhibitors of cytochrome P450 enzymes are unlikely.

Oral Contraceptives

In an open-label drug interaction study in healthy female volunteers, erenumab-aooe (140 mg subcutaneous, single-dose) did not affect the pharmacokinetics of a combined oral contraceptive containing ethinyl estradiol and norgestimate.

Sumatriptan

In a study in healthy volunteers, concomitant administration of erenumab-aooe with sumatriptan had no effect on the pharmacokinetics of sumatriptan [see Clinical Pharmacology (12.2)].

12.6 Immunogenicity

The observed incidence of anti-drug antibodies is highly dependent on the sensitivity and specificity of the assay. Differences in assay methods preclude meaningful comparisons of the incidence of anti-drug antibodies in the studies described below with the incidence of anti-drug antibodies in other studies, including those of erenumab-aooe.

The immunogenicity of AIMOVIG has been evaluated using an immunoassay for the detection of binding anti-erenumab-aooe antibodies. For patients whose sera tested positive in the screening immunoassay, an in vitro biological assay was performed to detect neutralizing antibodies.

In controlled studies with AIMOVIG [see Clinical Studies (14)], the incidence of anti-erenumab-aooe antibody development was 6.2% (48/778) in patients receiving AIMOVIG 70 mg once monthly (2 of whom had in vitro neutralizing activity) and 2.6% (13/504) in patients receiving AIMOVIG 140 mg once monthly (none of whom had in vitro neutralizing activity). In a long-term study, including 12 weeks of double-blind treatment and up to 256 weeks of open-label treatment, the incidence of anti-erenumab-aooe antibody development was 11.1% (25/225) among patients whose AIMOVIG dose was 70 mg or 140 mg (2 of whom had in vitro neutralizing activity). The neutralizing anti-erenumab-aooe antibody positive rate may be underestimated because of limitations of the assay. Although these data do not demonstrate an impact of anti-erenumab-aooe antibody development on the efficacy or safety of AIMOVIG in these patients, the available data are too limited to make definitive conclusions.

13 NONCLINICAL TOXICOLOGY

13.1 Carcinogenesis, Mutagenesis, Impairment of Fertility

Carcinogenesis

The carcinogenic potential of erenumab-aooe has not been assessed.

Mutagenesis

Genetic toxicology studies of erenumab-aooe have not been conducted.

Impairment of Fertility

Mating studies have not been conducted on erenumab-aooe. No histopathological changes in male or female reproductive organs were observed in monkeys administered erenumab-aooe (0, 25, or 150 mg/kg) by subcutaneous injection twice weekly for up to 6 months. Serum erenumab-aooe exposures (AUC) at the higher dose tested were more than 100 times that in humans at a dose of 140 mg once monthly.

14 CLINICAL STUDIES

The efficacy of AIMOVIG was evaluated as a preventive treatment of episodic or chronic migraine in three randomized, double-blind, placebo-controlled studies: two studies in patients with episodic migraine (4 to 14 migraine days per month) (Study 1 and Study 2) and one study in patients with chronic migraine (≥ 15 headache days per month with ≥ 8 migraine days per month) (Study 3). The studies enrolled patients with a history of migraine, with or without aura, according to the International Classification of Headache Disorders (ICHD-III) diagnostic criteria.

Episodic Migraine

Study 1 (NCT 02456740) was a randomized, multi-center, 6-month, placebo-controlled, double-blind study evaluating AIMOVIG for the preventive treatment of episodic migraine. A total of 955 patients with a history of episodic migraine were randomized to receive either AIMOVIG 70 mg (N = 317), AIMOVIG 140 mg (N = 319), or placebo (N = 319) by subcutaneous injection once monthly (QM) for 6 months. Patients were allowed to use acute headache treatments including migraine-specific medications (i.e., triptans, ergotamine derivatives) and NSAIDs during the study.

The study excluded patients with medication overuse headache as well as patients with myocardial infarction, stroke, transient ischemic attacks, unstable angina, coronary artery bypass surgery, or other revascularization procedures within 12 months prior to screening.

The primary efficacy endpoint was the change from baseline in mean monthly migraine days over months 4 to 6. Secondary endpoints included the achievement of a ≥ 50% reduction from baseline in mean monthly migraine days over months 4 to 6 ("≥ 50% MMD responders"), the change from baseline in mean monthly acute migraine-specific medication days over months 4 to 6, and the change from baseline in mean Migraine Physical Function Impact Diary (MPFID) over months 4 to 6. The MPFID measures the impact of migraine on everyday activities (EA) and physical impairment (PI) using an electronic diary administered daily. Monthly MPFID scores are averaged over 28 days, including days with and without migraine; scores are scaled from 0 to 100. Higher scores indicate worse impact on EA and PI. Reductions from baseline in MPFID scores indicate improvement.

A total of 858 (90%) patients completed the 6-month double-blind study. Patients had a median age of 42 years (range: 18 to 65 years), 85% were female, and 89% were white. Three percent of patients were taking concomitant preventive treatments for migraine. The mean migraine frequency at baseline was approximately 8 migraine days per month and was similar across treatment groups.

AIMOVIG treatment demonstrated statistically significant improvements for key efficacy endpoints compared to placebo, as summarized in Table 3.

Table 3: Efficacy Endpoints Over Months 4 to 6 in Study 1
 | AIMOVIG 70 mg Once Monthly | AIMOVIG 140 mg Once Monthly | Placebo
 | N = 312 | N = 318 | N = 316
Monthly Migraine Days (MMD)
Change from baseline | −3.2 | −3.7 | −1.8
Difference from placebo | −1.4 | −1.9
p-value | < 0.001 | < 0.001
≥ 50% MMD responders
% Responders | 43.3% | 50.0% | 26.6%
Difference from placebo | 16.7% | 23.4%
Odds ratio relative to placebo | 2.1 | 2.8
p-value | < 0.001 | < 0.001
Monthly acute migraine-specific medication days
Change from baseline | −1.1 | −1.6 | −0.2
Difference from placebo | −0.9 | −1.4
p-value | < 0.001 | < 0.001

Figure 1: Change from Baseline in Monthly Migraine Days in Study 1 [Least-square means and 95% confidence intervals are presented.]

Figure 2 shows the distribution of change from baseline in mean monthly migraine days over months 4 to 6 in bins of 2 days by treatment group. A treatment benefit over placebo for both doses of AIMOVIG is seen across a range of changes from baseline in monthly migraine days.

Figure 2: Distribution of Change from Baseline in Mean Monthly Migraine Days Over Months 4 to 6 by Treatment Group in Study 1

Figure excludes patients with missing data.

Compared to placebo, patients treated with AIMOVIG 70 mg once monthly and 140 mg once monthly showed greater reductions from baseline in mean monthly MPFID everyday activity scores averaged over months 4 to 6 [difference from placebo: −2.2 for AIMOVIG 70 mg and −2.6 for AIMOVIG 140 mg; p-value < 0.001 for both], and in mean monthly MPFID physical impairment scores averaged over months 4 to 6 [difference from placebo: −1.9 for AIMOVIG 70 mg and −2.4 for AIMOVIG 140 mg; p-value < 0.001 for both].

Study 2 (NCT 02483585) was a randomized, multi-center, 3-month, placebo-controlled, double-blind study evaluating AIMOVIG for the preventive treatment of episodic migraine. A total of 577 patients with a history of episodic migraine were randomized to receive either AIMOVIG 70 mg (N = 286) or placebo (N = 291) by subcutaneous injection once monthly for 3 months. Patients were allowed to use acute headache treatments including migraine-specific medications (i.e., triptans, ergotamine derivatives) and NSAIDs during the study.

The study excluded patients with medication overuse headache as well as patients with myocardial infarction, stroke, transient ischemic attacks, unstable angina, coronary artery bypass surgery, or other revascularization procedures within 12 months prior to screening.

The primary efficacy endpoint was the change from baseline in monthly migraine days at month 3. Secondary endpoints included the achievement of a ≥ 50% reduction from baseline in monthly migraine days ("≥ 50% MMD responders"), the change from baseline in monthly acute migraine-specific medication days at month 3, and the proportion of patients with at least a 5-point score reduction from baseline in MPFID at month 3.

A total of 546 (95%) patients completed the 3-month double-blind study. Patients had a median age of 43 years (range: 18 to 65 years), 85% were female, and 90% were white. Six to seven percent of patients were taking concomitant preventive migraine treatment. The mean migraine frequency at baseline was approximately 8 migraine days per month and was similar between treatment groups.

AIMOVIG treatment demonstrated statistically significant improvements for key efficacy endpoints compared to placebo, as summarized in Table 4.

Table 4: Efficacy Endpoints at Month 3 for Study 2
 | AIMOVIG 70 mg Once Monthly | Placebo
 | N = 282 | N = 288
Monthly Migraine Days (MMD)
Change from baseline | −2.9 | −1.8
Difference from placebo | −1.0
p-value | < 0.001
≥ 50% MMD responders
% Responders | 39.7% | 29.5%
Difference from placebo | 10.2%
Odds ratio relative to placebo | 1.6
p-value | 0.010
Monthly acute migraine-specific medication days
Change from baseline | −1.2 | −0.6
Difference from placebo | −0.6
p-value | 0.002

Figure 3: Change from Baseline in Monthly Migraine Days in Study 2 [Least-square means and 95% confidence intervals are presented.]

Figure 4 shows the distribution of change from baseline in monthly migraine days at month 3 in bins of 2 days by treatment group. A treatment benefit over placebo for AIMOVIG is seen across a range of changes from baseline in monthly migraine days.

Figure 4: Distribution of Change from Baseline in Monthly Migraine Days at Month 3 by Treatment Group in Study 2

Figure excludes patients with missing data.

The pre-specified analysis for the MPFID was based on at least a 5-point reduction within-patient responder definition. AIMOVIG 70 mg once monthly was not significantly better than placebo for the proportion of responders for everyday activity [difference from placebo: 4.7%; odds ratio = 1.2; p-value = 0.26] and physical impairment [difference from placebo: 5.9%; odds ratio = 1.3; p-value = 0.13]. In an exploratory analysis of the change from baseline in the mean MPFID scores at month 3, patients treated with AIMOVIG 70 mg, as compared to placebo, showed nominally greater reductions of physical impairment scores [difference from placebo: -1.3; p-value = 0.021], but not of everyday activities scores [difference from placebo: -1.1; p-value = 0.061].

Chronic Migraine

Study 3 (NCT 02066415) was a randomized, multi-center, 3-month, placebo-controlled, double-blind study evaluating AIMOVIG as a preventive treatment of chronic migraine. A total of 667 patients with a history of chronic migraine with or without aura were randomized to receive AIMOVIG 70 mg (N = 191), AIMOVIG 140 mg (N = 190), or placebo (N = 286) by subcutaneous injections once monthly for 3 months. Patients were allowed to use acute headache treatments including migraine-specific medications (i.e., triptans, ergotamine derivatives) and NSAIDs during the study.

The study excluded patients with medication overuse headache caused by opiate overuse and patients with concurrent use of migraine preventive treatments. Patients with myocardial infarction, stroke, transient ischemic attacks, unstable angina, coronary artery bypass surgery, or other revascularization procedures within 12 months prior to screening were also excluded.

The primary efficacy endpoint was the change from baseline in monthly migraine days at month 3. Secondary endpoints included the achievement of a ≥ 50% reduction from baseline in monthly migraine days ("≥ 50% MMD responders") and change from baseline in monthly acute migraine-specific medication days at month 3.

A total of 631 (95%) patients completed the 3-month double-blind study. Patients had a median age of 43 years (range: 18 to 66 years), 83% were female, and 94% were white. The mean migraine frequency at baseline was approximately 18 migraine days per month and was similar across treatment groups.

AIMOVIG treatment demonstrated statistically significant improvements for key efficacy outcomes compared to placebo, as summarized in Table 5.

Table 5: Efficacy Endpoints at Month 3 in Study 3
 | AIMOVIG 70 mg Once Monthly | AIMOVIG 140 mg Once Monthly | Placebo
 | N = 188 | N = 187 | N = 281
Monthly Migraine Days (MMD)
Change from baseline | −6.6 | −6.6 | −4.2
Difference from placebo | −2.5 | −2.5
p-value | < 0.001 | < 0.001
≥ 50% MMD responders
% Responders | 39.9% | 41.2% | 23.5%
Difference from placebo | 16.4% | 17.7%
Odds ratio relative to placebo | 2.2 | 2.3
p-value | < 0.001 | < 0.001
Monthly acute migraine-specific medication days
Change from baseline | −3.5 | −4.1 | −1.6
Difference from placebo | −1.9 | −2.6
p-value | < 0.001 | < 0.001

Figure 5: Change from Baseline in Monthly Migraine Days in Study 3 [Least-square means and 95% confidence intervals are presented.]

Figure 6 shows the distribution of change from baseline in monthly migraine days at month 3 in bins of 3 days by treatment group. A treatment benefit over placebo for both doses of AIMOVIG is seen across a range of changes from baseline in migraine days.

Figure 6: Distribution of Change from Baseline in Monthly Migraine Days at Month 3 by Treatment Group in Study 3

Figure excludes patients with missing data.

16 HOW SUPPLIED/STORAGE AND HANDLING

16.1 How Supplied

AIMOVIG (erenumab-aooe) injection is a sterile, clear to opalescent, colorless to light yellow solution for subcutaneous administration.

AIMOVIG prefilled autoinjectors and prefilled syringes are not made with natural rubber latex. Each single-dose prefilled SureClick® autoinjector or single-dose prefilled syringe of AIMOVIG contains a Type 1 glass syringe and stainless steel needle and delivers 1 mL of 70 mg/mL or 140 mg/mL solution.

AIMOVIG is supplied as follows:

SureClick® Autoinjector

- Pack of 1 autoinjector: 70 mg/mL single-dose prefilled autoinjector
  NDC 55513-841-01
- Pack of 1 autoinjector: 140 mg/mL single-dose prefilled autoinjector
  NDC 55513-843-01

Syringe

- Pack of 1 syringe: 70 mg/mL single-dose prefilled syringe
  NDC 55513-840-01
- Pack of 1 syringe: 140 mg/mL single-dose prefilled syringe
  NDC 55513-842-01

16.2 Storage and Handling

- Store refrigerated at 2°C to 8°C (36°F to 46°F) in the original carton to protect from light until time of use.
- If removed from the refrigerator, AIMOVIG should be kept at room temperature (up to 25°C [77°F]) in the original carton and must be used within 7 days. Throw away AIMOVIG that has been left at room temperature for more than 7 days.
- Do not freeze.
- Do not shake.

17 PATIENT COUNSELING INFORMATION

Advise the patient to read the FDA-approved patient labeling (Patient Information and Instructions for Use).

Information on Preparation and Administration

Provide guidance to patients and caregivers on proper subcutaneous administration technique, including aseptic technique, and how to use the single-dose prefilled autoinjector or single-dose prefilled syringe [see Dosage and Administration (2.2)]. Instruct patients and/or caregivers to read and follow the Instructions for Use each time they use AIMOVIG.

Advise patients to let AIMOVIG sit at room temperature for at least 30 minutes prior to administration [see Dosage and Administration (2.2)].

Hypersensitivity Reactions

Advise patients to seek immediate medical attention if they experience any symptoms of serious or severe hypersensitivity reactions [see Warnings and Precautions (5.1)].

Constipation with Serious Complications

Advise patients that constipation with serious complications can occur with AIMOVIG and that they should contact their healthcare providers if they experience severe constipation [see Warnings and Precautions (5.2)].

Hypertension

Advise patients that development of hypertension and worsening of pre-existing hypertension can occur with AIMOVIG and that they should contact their healthcare providers if they experience elevation in their blood pressure [see Warnings and Precautions (5.3)].

Pregnancy

Advise patients that there is a pregnancy exposure registry that monitors pregnancy outcomes in women exposed to AIMOVIG during pregnancy [see Use in Specific Populations (8.1)].

Raynaud's Phenomenon

Inform patients that Raynaud's phenomenon can develop or worsen with AIMOVIG. Advise patients to discontinue AIMOVIG and contact their healthcare provider if they experience signs or symptoms of Raynaud's phenomenon [see Warnings and Precautions (5.4)].

For more information, go to www.aimovig.com or call 1-800-77-AMGEN (1-800-772-6436).

AIMOVIG® (erenumab-aooe)

Manufactured by:
Amgen Inc.
One Amgen Center Drive
Thousand Oaks, CA 91320-1799 U.S.A.
U.S. License No. 1080

Patent: http://pat.amgen.com/aimovig/
© 2018-2025 Amgen Inc. All rights reserved.
[part number] V12

Patient Information
AIMOVIG® (AIM-oh-vig) (erenumab-aooe)
injection, for subcutaneous use

What is AIMOVIG?
AIMOVIG is a prescription medicine used for the preventive treatment of migraine in adults.
It is not known if AIMOVIG is safe and effective in children under 18 years of age.

Who should not use AIMOVIG?
Do not use AIMOVIG if you are allergic to erenumab-aooe or any of the ingredients in AIMOVIG. See the end of this Patient Information for a complete list of ingredients in AIMOVIG.

Before you start using AIMOVIG, tell your healthcare provider about all your medical conditions, including if you:

- have high blood pressure
- have circulation problems in your fingers and toes
- are pregnant or plan to become pregnant. It is not known if AIMOVIG will harm your unborn baby.
  - Pregnancy Registry: There is a pregnancy registry for women who take AIMOVIG. The purpose of this registry is to collect information about your health and your baby's health. You may enroll yourself by calling 1-833-244-4083 or visiting https://www.genesispregnancyregistry.com/. Or you may talk to your healthcare provider about how you can take part in this registry.
- are breastfeeding or plan to breastfeed. It is not known if AIMOVIG passes into your breast milk. Talk to your healthcare provider about the best way to feed your baby while using AIMOVIG.

Tell your pharmacist or healthcare provider about all the medicines you take, including any prescription and over-the-counter medicines, vitamins, or herbal supplements.

How should I take AIMOVIG?

- See the detailed "Instructions for Use" on complete information on how to take AIMOVIG.
- Take AIMOVIG exactly as your healthcare provider tells you to take it.
- Before you inject, always check the label of your single-dose prefilled autoinjector or single-dose prefilled syringe to make sure you have the correct medicine and the correct dose of AIMOVIG.
- Also, before you inject, leave AIMOVIG at room temperature for at least 30 minutes protected from direct sunlight.
- AIMOVIG is injected under your skin (subcutaneously) 1 time each month.
- AIMOVIG comes in 2 different types of devices: a single-dose (1 time) prefilled autoinjector or a single-dose (1 time) prefilled syringe. Your healthcare provider will prescribe the type and dose that is best for you.
- If you forget to take AIMOVIG or are not able to take the dose at the regular time, take your missed dose as soon as you remember. After that, you can continue to take AIMOVIG 1 time each month from the date of your last dose.

What are possible side effects of AIMOVIG?
AIMOVIG may cause serious side effects, including:

- Allergic reactions. Allergic reactions, including rash or swelling can happen after receiving AIMOVIG. This can happen within hours to days after using AIMOVIG. Call your healthcare provider or get emergency medical help right away if you have any of the following symptoms of an allergic reaction:
  - swelling of the face, mouth, tongue, or throat
  - trouble breathing
- Constipation with serious complications. Severe constipation can happen after receiving AIMOVIG. In some cases, people have been hospitalized or needed surgery. Contact your healthcare provider if you have severe constipation or constipation associated with symptoms such as severe or constant belly pain, vomiting, swelling of belly or bloating.
- High blood pressure. High blood pressure or worsening of high blood pressure can happen after receiving AIMOVIG. Contact your healthcare provider if you have an increase in blood pressure.
- Raynaud's phenomenon. A type of circulation problem can worsen or happen after receiving AIMOVIG. Raynaud's phenomenon can lead to your fingers or toes feeling numb, cool, or painful, or changing color from pale, to blue, to red. Contact your healthcare provider if these symptoms occur.

The most common side effects of AIMOVIG include: pain, redness, or swelling at the injection site and constipation.
Tell your healthcare provider if you have any side effect that bothers you or that does not go away.
These are not all of the possible side effects of AIMOVIG. Ask your pharmacist or healthcare provider for more information.
Call your healthcare provider for medical advice about side effects. You may report side effects to the FDA at 1-800-FDA-1088. You may also report side effects to Amgen at 1-800-77-AMGEN (1-800-772-6436).

How should I store AIMOVIG?

- Store AIMOVIG in the refrigerator between 36°F to 46°F (2°C to 8°C).
- Keep AIMOVIG in the original carton. This will protect the medicine from light.
- After removing AIMOVIG from the refrigerator, it can be stored at room temperature between 68°F to 77°F (20°C to 25°C) for up to 7 days.
- Throw away AIMOVIG that has been left at room temperature for more than 7 days.
- Do not freeze.
- Do not shake.

Keep AIMOVIG and all medicines out of the reach of children.

General information about the safe and effective use of AIMOVIG.
Medicines are sometimes prescribed for purposes other than those listed in a Patient Information leaflet. Do not use AIMOVIG for a condition for which it is not prescribed. Do not give AIMOVIG to other people, even if they have the same symptoms that you have. It can harm them. You can ask your pharmacist or healthcare provider for information about AIMOVIG that is written for healthcare professionals.

What are the ingredients in AIMOVIG?

- Active Ingredient: erenumab-aooe
- Inactive Ingredients: acetate, polysorbate 80, and sucrose

AIMOVIG prefilled autoinjectors and prefilled syringes are not made with natural rubber latex.

AIMOVIG® (erenumab-aooe)
Manufactured by:
Amgen Inc.
One Amgen Center Drive
Thousand Oaks, CA 91320-1799 U.S.A.
U.S. License No. 1080
Patent: http://pat.amgen.com/aimovig/
© 2018-2025 Amgen Inc. All rights reserved.
For more information, go to www.aimovig.com or call 1-800-77-AMGEN (1-800-772-6436).

This Patient Information has been approved by the U.S. Food and Drug Administration.
[part number] v10

Revised: 3/2025

INSTRUCTIONS FOR USE AIMOVIG® [AIM-oh-vig] (erenumab-aooe) injection, for subcutaneous use 70 mg/mL single-dose prefilled SureClick® autoinjector

This Instructions for Use contains information on how to inject AIMOVIG with a SureClick autoinjector.

If your healthcare provider decides that you or a caregiver may be able to give your injections of AIMOVIG at home, you should receive training on the right way to prepare and inject AIMOVIG. Do not try to inject yourself until you have been shown the right way to give the injections by your healthcare provider or nurse.

The medicine in the AIMOVIG autoinjector is for injection under the skin (subcutaneous injection). See the AIMOVIG Patient Information for information about AIMOVIG.

Getting to know your prefilled autoinjector

Important Information You Need to Know Before Injecting AIMOVIG

- It is important that you do not try to give the injection until you have fully read and understood this Instructions for Use.
- Check the autoinjector label and prescription to make sure you have the correct medicine and dose.
- Do not use the autoinjector if the carton is damaged or the seal is broken.
- Do not use the autoinjector after the expiration date on the label.
- Do not shake the autoinjector.
- Do not remove the white cap from the autoinjector until you are ready to inject.
- Do not use the autoinjector if it has been frozen.
- Do not use the autoinjector if it has been dropped on a hard surface. Part of the autoinjector may be broken even if you cannot see the break. Use a new autoinjector, and call 1-800-77-AMGEN (1-800-772-6436).
- The autoinjector is not made with natural rubber latex.

Frequently asked questions:
For additional information and answers to frequently asked questions, visit www.aimovig.com.

Where to get help:
If you want more information or help using AIMOVIG:

- Contact your healthcare provider,
- Visit www.aimovig.com, or
- Call 1-800-77-AMGEN (1-800-772-6436)

Storing and Preparing to Inject AIMOVIG

1 Refrigerate the autoinjector carton until you are ready to use it.

- Keep the autoinjector in the refrigerator between 36°F to 46°F (2°C to 8°C).
- Keep the autoinjector in the original carton to protect it from light or physical damage.
- Do not freeze the autoinjector.
- Do not store the autoinjector in extreme heat or cold. For example, avoid storing in your vehicle's glove box or trunk.

Important: Keep the autoinjector and all medicines out of the sight and reach of children.

WAIT

2 Wait 30 minutes for the autoinjector to reach room temperature.

- Let the autoinjector warm up naturally.
- Do not heat the autoinjector with hot water, a microwave, or direct sunlight.
- Do not shake the autoinjector at any time.
- Using the autoinjector at room temperature makes sure the full dose is delivered and allows for a more comfortable injection.

3 You may keep AIMOVIG at room temperature for up to 7 days, if needed.

- For example, when you are traveling, you may keep AIMOVIG at room temperature.
  - Keep it at room temperature between 68°F to 77°F (20°C to 25°C).
  - Do not put it back in the refrigerator.
  - Record the date you removed it from the refrigerator and use it within 7 days.

Important: Place the autoinjector in a sharps disposal container if it has reached room temperature and has not been used within 7 days.

4 Inspect the medicine. It should be clear and colorless to slightly yellow.

- It is okay to see air bubbles.
- Do not use the autoinjector if the medicine is cloudy, discolored, or contains flakes or particles.

Important: If the medicine is cloudy, discolored, contains flakes or particles, or if the autoinjector is damaged or expired, call 1-800-77-AMGEN (1-800-772-6436).

5 Check the expiration date (Exp.) and inspect the autoinjector for damage.

- Do not use the autoinjector if the expiration date has passed.
- Do not use the autoinjector if:
  - the white cap is missing or loose in carton.
  - it has cracks or broken parts, or
  - it has been dropped on a hard surface.

Getting Ready to Inject AIMOVIG

6 Gather and place the following items for your injection on a clean, flat, and well-lit surface:

- AIMOVIG autoinjector (room temperature),
- Sharps disposal container [see Completing the Injection and Disposal],
- Alcohol wipe,
- Adhesive bandage, and
- Cotton balls or gauze pads.

7 Select 1 of these injection sites.

- Select the thigh or stomach (except for 2 inches around the belly button).
- Someone else can inject in your thigh, stomach, or back of the upper arm.

Important: Avoid areas with scars or stretch marks, or where the skin is tender, bruised, red, hard, raised, thick or scaly skin patch, or lesion.

8 Wash your hands thoroughly with soap and water.

9 Clean the injection site with an alcohol wipe.

- Let the skin dry on its own.
- Do not touch this area again before injecting.

Injecting AIMOVIG

Important: Only remove the white cap when you can inject right away (within 5 minutes) because the medicine can dry out. Do not recap.

10 Grasp the autoinjector so you can see the window. Pull the white cap straight off. You may need to pull hard.

- Do not twist, bend, or wiggle the white cap to pull it off.
- Never put the white cap back on. It may damage the needle.
- Do not put your finger inside the dark green safety guard.
- It is normal to see a drop of medicine come out of the needle or dark green safety guard.

11 Stretch or pinch the skin to create a firm surface at the injection site until the injection is finished. Place the dark green safety guard straight against the skin.

- Make sure you can see the window.
- Make sure the autoinjector is positioned straight on the injection site (at a 90-degree angle).

PUSH
and hold against skin

12 Firmly push the autoinjector down until the dark green safety guard stops moving. Hold the autoinjector down, do not lift.

- The dark green safety guard pushes in and unlocks the purple start button.

PRESS
purple start button

13 Keep pushing the autoinjector down and press the purple start button to start the injection.

- You may hear or feel a click.
- The window starts to turn yellow.
- It is okay to let go of the purple start button.

WATCH
window will turn fully yellow

14 Keep pushing the autoinjector down. Wait for the window to turn fully yellow.

- The injection may take up to 15 seconds to complete.
- You may hear or feel a click.
- After the window turns fully yellow, lift the autoinjector away from the skin.
- The dark green safety guard locks around the needle.

Completing the Injection and Disposal

CONFIRM

15 Confirm a full dose of medicine was injected.

- Do not touch the dark green safety guard.
- A small drop of liquid on the injection site is okay.

Important: If the window has not turned fully yellow or if it looks like the medicine is still coming out, a full dose was not injected. Call your healthcare provider right away.

16 Check the injection site.

- Do not rub the injection site.
- If there is blood, press a cotton ball or gauze pad on your injection site.
- Apply an adhesive bandage if necessary.

For more information or help call 1-800-77-AMGEN (1-800-772-6436).

17 Place the used autoinjector and white cap in an FDA-cleared sharps disposal.

Important: Do not throw away the autoinjector in your household trash.

- Do not reuse the autoinjector.
- Do not touch the dark green safety guard.

Additional information about your sharps disposal container
If you do not have an FDA-cleared sharps disposal container, you may use a household container that is:

- made of a heavy-duty plastic,
- can be closed with a tight-fitting, puncture-resistant lid, without sharps being able to come out,
- upright and stable during use,
- leak-resistant, and
- properly labeled to warn of hazardous waste inside the container.

Disposing of sharps disposal containers:

When your sharps disposal container is almost full, you will need to follow your community guidelines for the right way to dispose of your sharps disposal container.

There may be state or local laws about how you should throw away used needles and syringes.

For more information about safe sharps disposal, and for specific information about sharps disposal in the state that you live in, go to the FDA's website at:

http://www.fda.gov/safesharpsdisposal

Do not dispose of your used sharps disposal container in your household trash unless your community guidelines permit this.

Do not recycle your used sharps disposal container.

Keep the autoinjector and sharps disposal container out of the sight and reach of children.

AIMOVIG® (AIM-oh-vig)

Manufactured by:
Amgen Inc.
One Amgen Center Drive
Thousand Oaks, California 91320-1799
U.S. License Number 1080

© 2018 – 2025 Amgen Inc.
All rights reserved.
1XXXXXX

This Instructions for Use has been approved by the U.S. Food and Drug Administration.

Revised: 6/2025
v12

REFERENCE GUIDE
Side 1 | Reference Guide Aimovig® [AIM-oh-vig] (erenumab-aooe) injection, for subcutaneous use 70 mg/mL |  |  | Read instructions for Use in carton before injecting Questions? Call 1-800-77-AMGEN (1-800-772-6436)
1. | Guide to parts | 2. | Wait 30 minutes for the autoinjector to reach room temperature before giving your injection. | 3. | Prepare and clean your injection site. | 4. | Pull the white cap straight off when you are ready to inject within 5 minutes − the medicine can dry out.
 |  | WAIT
 |  |  |  |  |  |  | Turn over to continue

Side 2 | Reference Guide Aimovig® [AIM-oh-vig] (erenumab-aooe) injection, for subcutaneous use 70 mg/mL |  |  | Manufactured by: Amgen, Inc. Thousand Oaks, CA 91320 © 2020-2022, 2024 – 2025 Amgen Inc. All rights reserved. <part number> Revised: 6/2025 v5 |  | Read other side first
Side 2 | Reference Guide Aimovig® [AIM-oh-vig] (erenumab-aooe) injection, for subcutaneous use 70 mg/mL |  |  | Manufactured by: Amgen, Inc. Thousand Oaks, CA 91320 © 2020-2022, 2024 – 2025 Amgen Inc. All rights reserved. <part number> Revised: 6/2025 v5 |  | This printed material is recyclable.
5. | Stretch or pinch the skin to create a firm surface at the injection site until the injection is finished. | 6. | PUSH and HOLD down against the skin. Do not lift. | 7. | PRESS purple start button | 8. | Keep pushing down for up to 15 seconds. Wait for the window to turn fully yellow, then your injection is done.

INSTRUCTIONS FOR USE AIMOVIG® [AIM-oh-vig] (erenumab-aooe) injection, for subcutaneous use 140 mg/mL single-dose prefilled SureClick® autoinjector

This Instructions for Use contains information on how to inject AIMOVIG with a SureClick autoinjector.

If your healthcare provider decides that you or a caregiver may be able to give your injections of AIMOVIG at home, you should receive training on the right way to prepare and inject AIMOVIG. Do not try to inject yourself until you have been shown the right way to give the injections by your healthcare provider or nurse.

The medicine in the AIMOVIG autoinjector is for injection under the skin (subcutaneous injection). See the AIMOVIG Patient Information for information about AIMOVIG.

Getting to know your prefilled autoinjector

Important Information You Need to Know Before Injecting AIMOVIG

- It is important that you do not try to give the injection until you have fully read and understood this Instructions for Use.
- Check the autoinjector label and prescription to make sure you have the correct medicine and dose.
- Do not use the autoinjector if the carton is damaged or the seal is broken.
- Do not use the autoinjector after the expiration date on the label.
- Do not shake the autoinjector.
- Do not remove the orange cap from the autoinjector until you are ready to inject.
- Do not use the autoinjector if it has been frozen.
- Do not use the autoinjector if it has been dropped on a hard surface. Part of the autoinjector may be broken even if you cannot see the break. Use a new autoinjector, and call 1-800-77-AMGEN (1-800-772-6436).
- The autoinjector is not made with natural rubber latex.

Frequently asked questions:
For additional information and answers to frequently asked questions, visit www.aimovig.com.

Where to get help:
If you want more information or help using AIMOVIG:

- Contact your healthcare provider,
- Visit www.aimovig.com, or
- Call 1-800-77-AMGEN (1-800-772-6436)

Storing and Preparing to Inject AIMOVIG

1 Refrigerate the autoinjector carton until you are ready to use it.

- Keep the autoinjector in the refrigerator between 36°F to 46°F (2°C to 8°C).
- Keep the autoinjector in the original carton to protect it from light or physical damage.
- Do not freeze the autoinjector.
- Do not store the autoinjector in extreme heat or cold. For example, avoid storing in your vehicle's glove box or trunk.

Important: Keep the autoinjector and all medicines out of the sight and reach of children.

WAIT

2 Wait 30 minutes for the autoinjector to reach room temperature.

- Let the autoinjector warm up naturally.
- Do not heat the autoinjector with hot water, a microwave, or direct sunlight.
- Do not shake the autoinjector at any time.
- Using the autoinjector at room temperature makes sure the full dose is delivered and allows for a more comfortable injection.

3 You may keep AIMOVIG at room temperature for up to 7 days, if needed.

- For example, when you are traveling, you may keep AIMOVIG at room temperature.
  - Keep it at room temperature between 68°F to 77°F (20°C to 25°C).
  - Do not put it back in the refrigerator.
  - Record the date you removed it from the refrigerator and use it within 7 days.

Important: Place the autoinjector in a sharps disposal container if it has reached room temperature and has not been used within 7 days.

4 Inspect the medicine. It should be clear and colorless to slightly yellow.

- It is okay to see air bubbles.
- Do not use the autoinjector if the medicine is cloudy, discolored, or contains flakes or particles.

Important: If the medicine is cloudy, discolored, or contains flakes or particles, or if the autoinjector is damaged or expired, call 1-800-77-AMGEN (1-800-772-6436).

5 Check the expiration date (Exp.) and inspect the autoinjector for damage.

- Do not use the autoinjector if the expiration date has passed.
- Do not use the autoinjector if:
  - the orange cap is missing or loose in carton.
  - it has cracks or broken parts, or
  - it has been dropped on a hard surface.

Getting Ready to Inject AIMOVIG

6 Gather and place the following items for your injection on a clean, flat, and well-lit surface:

- AIMOVIG autoinjector (room temperature),
- Sharps disposal container [see Completing the Injection and Disposal],
- Alcohol wipe,
- Adhesive bandage, and
- Cotton balls or gauze pads

7 Select 1 of these injection sites.

- Select the thigh or stomach (except for 2 inches around the belly button).
- Someone else can inject in your thigh, stomach, or back of the upper arm.

Important: Avoid areas with scars or stretch marks, or where the skin is tender, bruised, red, hard, raised, thick or scaly skin patch, or lesion.

8 Wash your hands thoroughly with soap and water.

9 Clean the injection site with an alcohol wipe.

- Let the skin dry on its own.
- Do not touch this area again before injecting.

Injecting AIMOVIG

Important: Only remove the orange cap when you can inject right away (within 5 minutes) because the medicine can dry out. Do not recap.

10 Grasp the autoinjector so you can see the window. Pull the orange cap straight off. You may need to pull hard.

- Do not twist, bend, or wiggle the orange cap to pull it off.
- Never put the orange cap back on. It may damage the needle.
- Do not put your finger inside the yellow safety guard.
- It is normal to see a drop of medicine come out of the needle or yellow safety guard.

11 Stretch or pinch the skin to create a firm surface at the injection site until the injection is finished. Place the yellow safety guard straight against the skin.

- Make sure you can see the window.
- Make sure the autoinjector is positioned straight on the injection site (at a 90-degree angle).

PUSH
and hold against skin

12 Firmly push the autoinjector down until the yellow safety guard stops moving. Hold the autoinjector down, do not lift.

- The yellow safety guard pushes in and unlocks the gray start button.

PRESS
gray start button

13 Keep pushing the autoinjector down and press the gray start button to start the injection.

- You may hear or feel a click.
- The window starts to turn yellow.
- It is okay to let go of the gray start button.

WATCH
window will turn fully yellow

14 Keep pushing the autoinjector down. Wait for the window to turn fully yellow.

- The injection may take up to 15 seconds to complete.
- You may hear or feel a click.
- After the window turns fully yellow, lift the autoinjector away from the skin.
- The yellow safety guard locks around the needle.

Completing the Injection and Disposal

CONFIRM

15 Confirm a full dose of medicine was injected.

- Do not touch the yellow safety guard.
- A small drop of liquid on the injection site is okay.

Important: If the window has not turned fully yellow or if it looks like the medicine is still coming out, a full dose was not injected. Call your healthcare provider right away.

16 Check the injection site.

- Do not rub the injection site.
- If there is blood, press a cotton ball or gauze pad on your injection site.
- Apply an adhesive bandage if necessary.

For more information or help call 1-800-77-AMGEN (1-800-772-6436).

17 Place the used autoinjector and orange cap in an FDA-cleared sharps disposal.

Important: Do not throw away the autoinjector in your household trash.

- Do not reuse the autoinjector.
- Do not touch the yellow safety guard.

Additional information about your sharps disposal container
If you do not have an FDA-cleared sharps disposal container, you may use a household container that is:

- made of a heavy-duty plastic,
- can be closed with a tight-fitting, puncture-resistant lid, without sharps being able to come out,
- upright and stable during use,
- leak-resistant, and
- properly labeled to warn of hazardous waste inside the container.

Disposing of sharps disposal containers:

When your sharps disposal container is almost full, you will need to follow your community guidelines for the right way to dispose of your sharps disposal container.

There may be state or local laws about how you should throw away used needles and syringes.

For more information about safe sharps disposal, and for specific information about sharps disposal in the state that you live in, go to the FDA's website at:

http://www.fda.gov/safesharpsdisposal

Do not dispose of your used sharps disposal container in your household trash unless your community guidelines permit this.

Do not recycle your used sharps disposal container.

Keep the autoinjector and sharps disposal container out of the sight and reach of children.

AIMOVIG® (AIM-oh-vig)

Manufactured by:
Amgen Inc.
One Amgen Center Drive
Thousand Oaks, California 91320-1799
U.S. License Number 1080
© 2019 – 2025 Amgen Inc. All rights reserved.
1XXXXXX

This Instructions for Use has been approved by the U.S. Food and Drug Administration.

Revised: 6/2025
V11

REFERENCE GUIDE
Side 1 | Reference Guide Aimovig® [AIM-oh-vig] (erenumab-aooe) injection, for subcutaneous use 140 mg/mL |  |  | Read instructions for Use in carton before injecting Questions? Call 1-800-77-AMGEN (1-800-772-6436)
1. | Guide to parts | 2. | Wait 30 minutes for the autoinjector to reach room temperature before giving your injection. | 3. | Prepare and clean your injection site. | 4. | Pull the orange cap straight off when you are ready to inject within 5 minutes – the medicine can dry out.
 |  | WAIT
 |  |  |  |  |  |  | Turn over to continue

Side 2 | Reference Guide Aimovig® [AIM-oh-vig] (erenumab-aooe) injection, for subcutaneous use 140 mg/mL |  |  | Manufactured by: Amgen, Inc. Thousand Oaks, CA 91320 © 2020-2022, 2024 – 2025 Amgen Inc. All rights reserved. <part number> Revised: 6/2025 v5 |  | Read other side first
Side 2 | Reference Guide Aimovig® [AIM-oh-vig] (erenumab-aooe) injection, for subcutaneous use 140 mg/mL |  |  | Manufactured by: Amgen, Inc. Thousand Oaks, CA 91320 © 2020-2022, 2024 – 2025 Amgen Inc. All rights reserved. <part number> Revised: 6/2025 v5 |  | This printed material is recyclable.
5. | Stretch or pinch the skin to create a firm surface at the injection site until the injection is finished. | 6. | PUSH and HOLD down against the skin. Do not lift. | 7. | PRESS gray start button | 8. | Keep pushing down for up to 15 seconds. Wait for the window to turn fully yellow, then your injection is done.

Instructions for Use AIMOVIG® (AIM-oh-vig) (erenumab-aooe) Injection, For Subcutaneous Use Single-Dose Prefilled Syringe 70 mg/mL and 140 mg/mL

Important: Needle is inside the gray needle cap.

Important

Before you use AIMOVIG prefilled syringe, read this important information:

Storing your AIMOVIG prefilled syringe

- Keep the syringe out of the reach of children.
- Keep the syringe in the original carton to protect from light.
- The syringe should be kept in the refrigerator at 36°F to 46°F (2°C to 8°C).
- After removing AIMOVIG from the refrigerator, it can be stored at room temperature between 68°F to 77°F (20°C to 25°C) for up to 7 days.
- Throw away AIMOVIG that has been left at room temperature for more than 7 days.
- Do not freeze.

Using your AIMOVIG prefilled syringe

- It is important that you do not try to give the injection unless you or your caregiver has received training from your healthcare provider.
- Do not use a syringe after the expiration date on the label.
- Do not shake the syringe.
- Do not remove the gray needle cap from the syringe until you are ready to inject.
- Do not use the syringe if it has been frozen.
- Do not use a syringe if it has been dropped on a hard surface. Part of the syringe may be broken even if you cannot see the break. Use a new syringe, and call 1-800-77-AMGEN (1-800-772-6436).
- The prefilled syringe is not made with natural rubber latex.

Step 1: Prepare

AIMOVIG comes as a single-dose (1 time) prefilled syringe. Your healthcare provider will prescribe the dose that is best for you.

Before you inject, always check the label of your single-dose prefilled syringe to make sure you have the correct medicine and the correct dose of AIMOVIG.

A Remove AIMOVIG prefilled syringe from the carton.

Grab the syringe barrel to remove the syringe from the tray.

Place finger or thumb on edge of tray to secure it while you remove the syringe.

Grab Here

For safety reasons:

- Do not grab the plunger rod.
- Do not grab the gray needle cap.
- Do not remove the gray needle cap until you are ready to inject.
- Do not remove the finger flange. This is part of the syringe.

Leave the syringe at room temperature for at least 30 minutes before injecting.

- Do not put the syringe back in the refrigerator after it has reached room temperature.
- Do not try to warm the syringe by using a heat source such as hot water or microwave.
- Do not leave the syringe in direct sunlight.
- Do not shake the syringe.

Important: Always hold the prefilled syringe by the syringe barrel.

B Inspect the AIMOVIG prefilled syringe.

Always hold the syringe by the syringe barrel.

Make sure the medicine in the syringe is clear and colorless to slightly yellow.

- Do not use the syringe if the medicine is cloudy or discolored or contains flakes or particles.
- Do not use the syringe if any part appears cracked or broken.
- Do not use the syringe if the syringe has been dropped.
- Do not use the syringe if the gray needle cap is missing or not securely attached.
- Do not use the syringe if the expiration date printed on the label has passed.

In all cases, use a new syringe, and call 1-800-77-AMGEN (1-800-772-6436).

C Gather all materials needed for your injection.

Wash your hands thoroughly with soap and water.

On a clean, well-lit work surface, place the:

- New syringe
- Alcohol wipes
- Cotton balls or gauze pads
- Adhesive bandages
- Sharps disposal container

D Prepare and clean your injection site.

Only use these injection sites:

- Your thigh
- Stomach area (abdomen), except for a two inch area right around your navel
- Outer area of upper arm (only if someone else is giving you the injection)

Clean your injection site with an alcohol wipe. Let your skin dry.

- Do not touch this area again before injecting.
- Do not inject into areas where the skin is tender, bruised, red, or hard. Avoid injecting directly into raised, thick, red, or scaly skin patch or lesion, or areas with scars or stretch marks.

Step 2: Get ready

E Pull gray needle cap straight out and away from your body, only when you are ready to inject. Do not leave the gray needle cap off for more than five minutes. This can dry out the medicine.

It is normal to see a drop of liquid at the end of the needle.

- Do not twist or bend the gray needle cap.
- Do not put the gray needle cap back onto the syringe.
- Do not remove the gray needle cap from the syringe until you are ready to inject.

Important: Throw the gray needle cap into the sharps disposal container.

F Pinch your injection site to create a firm surface.

Pinch skin firmly between your thumb and fingers, creating an area about two inches wide.

Important: Keep skin pinched while injecting.

Step 3: Inject

G Hold the pinch. With the gray needle cap off, insert the syringe into your skin at 45 to 90 degrees.

Do not place your finger on the plunger rod while inserting the needle.

H Place your finger on the plunger rod. Using slow and constant pressure, push the plunger rod all the way down until the prefilled syringe stops moving.

I When done, release your thumb, and gently lift the syringe off of your skin.

Important: When you remove the syringe, if it looks like the medicine is still in the syringe barrel, this means you have not received a full dose. Call your healthcare provider immediately.

Step 4: Finish

J Discard the used syringe and the gray needle cap.

Put the used AIMOVIG syringe and gray needle cap in a FDA-cleared sharps disposal container right away after use. Do not throw away (dispose of) the syringe in your household trash.

If you do not have a FDA-cleared sharps disposal container, you may use a household container that is:

- Made of a heavy-duty plastic
- Can be closed with a tight-fitting, puncture-resistant lid, without sharps being able to come out
- Upright and stable during use
- Leak-resistant
- Properly labeled to warn of hazardous waste inside the container

When your sharps disposal container is almost full, you will need to follow your community guidelines for the right way to dispose of your sharps disposal container. There may be state or local laws about how you should throw away used needles and syringes. For more information about safe sharps disposal, and for specific information about sharps disposal in the state that you live in, go to the FDA's website at: http://www.fda.gov/safesharpsdisposal.

- Do not reuse the syringe.
- Do not recycle the syringe or sharps disposal container or throw them into household trash.

Important: Always keep the sharps disposal container out of the reach of children.

K Examine the injection site.

If there is blood, press a cotton ball or gauze pad on your injection site. Do not rub the injection site. Apply an adhesive bandage if needed.

For more information, go to www.aimovig.com or call 1-800-77-AMGEN (1-800-772-6436).

AIMOVIG® (erenumab-aooe)

Manufactured by:
Amgen Inc.
One Amgen Center Drive
Thousand Oaks, CA 91320-1799 USA
U.S. License No. 1080

© 2018-2022, 2024 Amgen Inc. All rights reserved.

Symbol table

Do not reuse

CAUTION, Prior to use, read the enclosed Instructions For Use for administration information and see package insert for full Prescribing Information

Lot number

This Instructions for Use has been approved by the U.S. Food and Drug Administration.
Approved: 8/2024
[partnumber] v7

PRINCIPAL DISPLAY PANEL - 70 mg/mL Syringe Carton

AMGEN®

1 x 70 mg/mL Prefilled Syringe
NDC 55513-840-01
Rx Only

aimovig®
(erenumab-aooe)
Injection

70
mg/mL

70 mg/mL

Single-dose Prefilled Syringe

For Subcutaneous Use Only

Store refrigerated at 2°C to 8°C (36°F to 46°F) in original
carton to protect from light. Do Not Freeze. Do Not Shake.

Before injecting, allow AIMOVIG to sit
at room temperature for at least 30 minutes
with cap on, protected from direct sunlight.

Keep out of the sight and reach of children.

For more information, go to Aimovig.com or
call 1-800-77-AMGEN (1-800-772-6436).

CAUTION, Prior to use,
read the enclosed
Instructions for Use for
administration information
and see package insert for
full Prescribing
Information

Do Not Reuse

Not made with
natural rubber latex

PRINCIPAL DISPLAY PANEL - 70 mg/mL Autoinjector Carton

1 x 70 mg/mL Prefilled Autoinjector
NDC 55513-841-01

aimovig®
(erenumab-aooe)
Injection

70
mg/mL

Aimovig.com/demo

70 mg/mL

Prefilled Autoinjector

For Subcutaneous Use Only

Store carton in refrigerator at 36°F to 46°F (2°C to 8°C).

Do Not Freeze or Shake.

Store in Carton to Protect from Light. Discard Any
Unused Portion.

Keep out of the sight and reach of children.

Not made with natural rubber latex

No U.S. standard of potency

CAUTION, Consult
Accompanying Documents

Do not re-use

Refrigerate
until ready
to use

Rx Only

AMGEN

PRINCIPAL DISPLAY PANEL - 70 mg/mL Autoinjector Carton - Not for Sale

1 x 70 mg/mL Prefilled Autoinjector
NDC 55513-841-00

aimovig®
(erenumab-aooe)
Injection

70
mg/mL

Aimovig.com/demo

70 mg/mL

Not for Sale

Prefilled Autoinjector

For Subcutaneous Use Only

Store carton in refrigerator at 36°F to 46°F (2°C to 8°C).

Do Not Freeze or Shake.

Store in Carton to Protect from Light. Discard Any
Unused Portion.

Keep out of the sight and reach of children.

Not made with natural rubber latex

No U.S. standard of potency

CAUTION, Consult
Accompanying Documents

Do not re-use

Refrigerate
until ready
to use

Rx Only

AMGEN

PRINCIPAL DISPLAY PANEL - 140 mg/mL Autoinjector Carton

1 x 140 mg/mL Prefilled Autoinjector
NDC 55513-843-01

aimovig®
(erenumab-aooe)
Injection

140
mg/mL

Aimovig.com/demo

140 mg/mL

Prefilled Autoinjector

For Subcutaneous Use Only

Store carton in refrigerator at 36°F to 46°F (2°C to 8°C).

Do Not Freeze or Shake.

Store in Carton to Protect from Light. Discard Any
Unused Portion.

Keep out of the sight and reach of children.

Not made with natural rubber latex

No U.S. standard of potency

CAUTION, Consult
Accompanying Documents

Do not re-use

Refrigerate
until ready
to use

Rx Only

AMGEN

PRINCIPAL DISPLAY PANEL - 140 mg/mL Autoinjector Carton - Not for Sale

1 x 140 mg/mL Prefilled Autoinjector
NDC 55513-843-00

aimovig®
(erenumab-aooe)
Injection

140
mg/mL

Aimovig.com/demo

140 mg/mL

Prefilled Autoinjector

Not for Sale

For Subcutaneous Use Only

Store carton in refrigerator at 36°F to 46°F (2°C to 8°C).

Do Not Freeze or Shake.

Store in Carton to Protect from Light. Discard Any
Unused Portion.

Keep out of the sight and reach of children.

Not made with natural rubber latex

No U.S. standard of potency

CAUTION, Consult
Accompanying Documents

Do not re-use

Refrigerate
until ready
to use

Rx Only

AMGEN

PRINCIPAL DISPLAY PANEL - 140 mg/mL Syringe Carton

AMGEN®

1 x 140 mg/mL Prefilled Syringe
NDC 55513-842-01
Rx Only

aimovig®
(erenumab-aooe)
Injection

140
mg/mL = 1
dose

140 mg/mL

Single-dose Prefilled Syringe

For Subcutaneous Use Only

Store refrigerated at 2°C to 8°C (36°F to 46°F) in original
carton to protect from light. Do Not Freeze. Do Not Shake.

Before injecting, allow AIMOVIG to sit at
room temperature for at least 30 minutes
with cap on, protected from direct sunlight.

Keep out of the sight and reach of children.

For more information, go to Aimovig.com or
call 1-800-77-AMGEN (1-800-772-6436).

CAUTION, Prior to use,
read the enclosed
Instructions for Use for
administration information
and see package insert for
full Prescribing Information

Do Not Reuse

Not made with
natural rubber latex